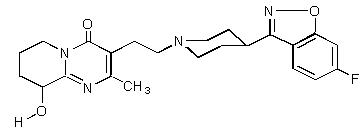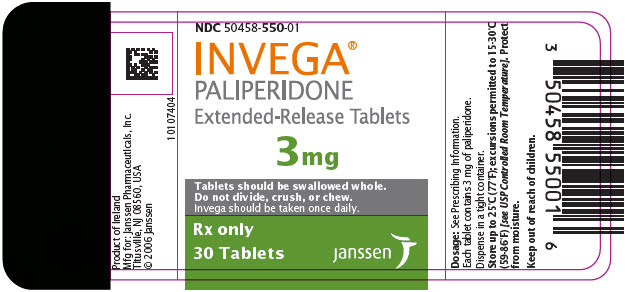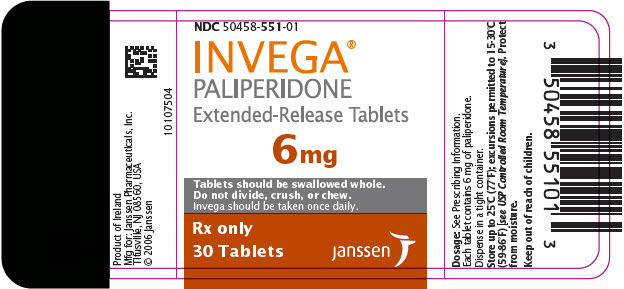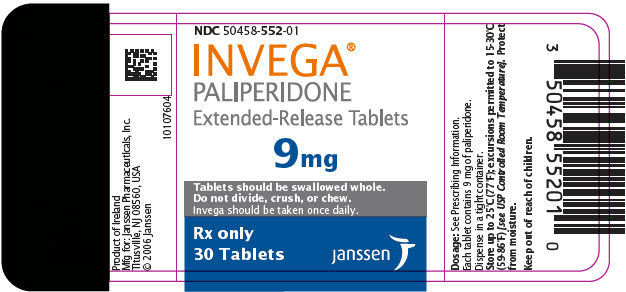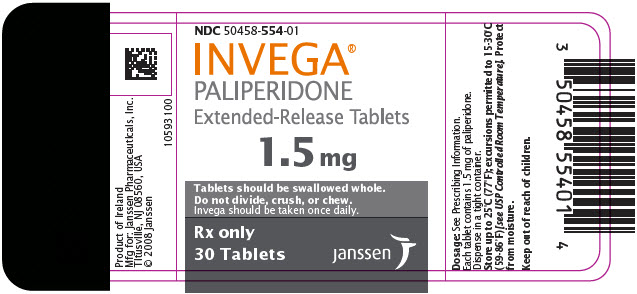 DRUG LABEL: INVEGA
NDC: 50458-550 | Form: TABLET, EXTENDED RELEASE
Manufacturer: Janssen Pharmaceuticals, Inc.
Category: prescription | Type: HUMAN PRESCRIPTION DRUG LABEL
Date: 20250206

ACTIVE INGREDIENTS: PALIPERIDONE 3 mg/1 1
INACTIVE INGREDIENTS: CARNAUBA WAX; CELLULOSE ACETATE; POLYETHYLENE GLYCOL, UNSPECIFIED; PROPYLENE GLYCOL; POVIDONE, UNSPECIFIED; SODIUM CHLORIDE; STEARIC ACID; BUTYLATED HYDROXYTOLUENE; HYPROMELLOSE, UNSPECIFIED; TITANIUM DIOXIDE; FERROSOFERRIC OXIDE; TRIACETIN; LACTOSE MONOHYDRATE

HIGHLIGHTS OF PRESCRIBING INFORMATION

These highlights do not include all the information needed to use INVEGA® safely and effectively. See full prescribing information for INVEGA®.
INVEGA® (paliperidone) Extended-Release Tablets
Initial U.S. Approval: 2006

WARNING: INCREASED MORTALITY IN ELDERLY PATIENTS WITH DEMENTIA-RELATED PSYCHOSIS

See full prescribing information for complete boxed warning.

Elderly patients with dementia-related psychosis treated with antipsychotic drugs are at an increased risk of death. INVEGA is not approved for use in patients with dementia-related psychosis. (5.1)

RECENT MAJOR CHANGES

Dosage and Administration (2.5) | 1/2025
Warnings and Precautions (5.7) | 1/2025

1 INDICATIONS AND USAGE

INVEGA is an atypical antipsychotic agent indicated for

Treatment of schizophrenia (1.1)

- Adults: Efficacy was established in three 6-week trials and one maintenance trial. (14.1)
- Adolescents (ages 12–17): Efficacy was established in one 6-week trial. (14.1)

Treatment of schizoaffective disorder as monotherapy and as an adjunct to mood stabilizers and/or antidepressants. (1.2)

- Efficacy was established in two 6-week trials in adult patients. (14.2)

2 DOSAGE AND ADMINISTRATION

 |  | Initial Dose | Recommended Dose | Maximum Dose
Schizophrenia - adults (2.1) |  | 6 mg/day | 3 – 12 mg/day | 12 mg/day
Schizophrenia-adolescents (2.1) | Weight < 51kg | 3 mg/day | 3 – 6 mg/day | 6 mg/day
Schizophrenia-adolescents (2.1) | Weight ≥ 51kg | 3 mg/day | 3 – 12 mg/day | 12 mg/day
Schizoaffective disorder - adults (2.2) |  | 6 mg/day | 3 – 12 mg/day | 12 mg/day

- Tablet should be swallowed whole and should not be chewed, divided, or crushed. (2.3)

3 DOSAGE FORMS AND STRENGTHS

Tablets: 3 mg, 6 mg, and 9 mg (3)

4 CONTRAINDICATIONS

Known hypersensitivity to paliperidone, risperidone, or to any excipients in INVEGA. (4)

5 WARNINGS AND PRECAUTIONS

- Cerebrovascular Adverse Reactions: An increased incidence of cerebrovascular adverse reactions (e.g. stroke, transient ischemic attack, including fatalities) has been seen in elderly patients with dementia- related psychoses treated with atypical antipsychotics. (5.2)
- Neuroleptic Malignant Syndrome: Manage with immediate discontinuation of drug and close monitoring. (5.3)
- QT Prolongation: Increase in QT interval, avoid use with drugs that also increase QT interval and in patients with risk factors for prolonged QT interval. (5.4)
- Tardive Dyskinesia: Discontinue drug if clinically appropriate. (5.5)
- Metabolic Changes: Atypical antipsychotic drugs have been associated with metabolic changes that may increase cardiovascular/ cerebrovascular risk. These metabolic changes include hyperglycemia, dyslipidemia, and weight gain. (5.6)
  - Hyperglycemia and Diabetes Mellitus: Monitor patients for symptoms of hyperglycemia including polydipsia, polyuria, polyphagia, and weakness. Monitor glucose regularly in patients with diabetes or at risk for diabetes. (5.6)
  - Dyslipidemia: Undesirable alterations have been observed in patients treated with atypical antipsychotics. (5.6)
  - Weight Gain: Significant weight gain has been reported. Monitor weight gain. (5.6)
- Hyperprolactinemia: Prolactin elevations occur and persist during chronic administration. (5.7)
- Gastrointestinal Narrowing: Obstructive symptoms may result in patients with gastrointestinal disease. (5.8)
- Orthostatic Hypotension and Syncope: Use with caution in patients with known cardiovascular or cerebrovascular disease and patients predisposed to hypotension. (5.9)
- Leukopenia, Neutropenia, and Agranulocytosis: has been reported with antipsychotics, including INVEGA. Patients with a history of a clinically significant low white blood cell count (WBC) or a drug-induced leukopenia/neutropenia should have their complete blood count (CBC) monitored frequently during the first few months of therapy and discontinuation of INVEGA should be considered at the first sign of a clinically significant decline in WBC in the absence of other causative factors. (5.11)
- Potential for Cognitive and Motor Impairment: Use caution when operating machinery. (5.12)
- Seizures: Use cautiously in patients with a history of seizures or with conditions that lower the seizure threshold. (5.13)

6 ADVERSE REACTIONS

Commonly observed adverse reactions (incidence ≥ 5% and at least twice that for placebo) were (6)

- Adults with schizophrenia: extrapyramidal symptoms, tachycardia, and akathisia.
- Adolescents with schizophrenia: somnolence, akathisia, tremor, dystonia, cogwheel rigidity, anxiety, weight increased, and tachycardia.
- Adults with schizoaffective disorder: extrapyramidal symptoms, somnolence, dyspepsia, constipation, weight increased, and nasopharyngitis.

To report SUSPECTED ADVERSE REACTIONS, contact Janssen Pharmaceuticals, Inc. at 1-800-526-7736 or FDA at 1-800-FDA-1088 or www.fda.gov/medwatch

7 DRUG INTERACTIONS

- Centrally-acting drugs: Due to CNS effects, use caution in combination. Avoid alcohol. (7.1)
- Drugs that may cause orthostatic hypotension: An additive effect may be observed when co-administered with INVEGA. (7.1)
- Strong CYP3A4/P-glycoprotein (P-gp) inducers: It may be necessary to increase the dose of INVEGA when a strong inducer of both CYP3A4 and P-gp (e.g., carbamazepine) is co-administered. Conversely, on discontinuation of the strong inducer, it may be necessary to decrease the dose of INVEGA. (7.2)
- Co-administration of divalproex sodium increased Cmax and AUC of paliperidone by approximately 50%. Adjust dose of INVEGA if necessary based on clinical assessment. (7.2)

8 USE IN SPECIFIC POPULATIONS

- Renal impairment: Dosing must be individualized according to renal function status. (2.5)
- Elderly: Same as for younger adults (adjust dose according to renal function status). (2.5)
- Pregnancy: May cause extrapyramidal and/or withdrawal symptoms in neonates with third trimester exposure. (8.1)
- Pediatric Use: Safety and effectiveness in the treatment of schizophrenia not established in patients less than 12 years of age. Safety and effectiveness in the treatment of schizoaffective disorder not established in patients less than 18 years of age. (8.4)

FULL PRESCRIBING INFORMATION

WARNING: INCREASED MORTALITY IN ELDERLY PATIENTS WITH DEMENTIA-RELATED PSYCHOSIS

Elderly patients with dementia-related psychosis treated with antipsychotic drugs are at an increased risk of death. INVEGA is not approved for the treatment of patients with dementia-related psychosis. [see Warnings and Precautions (5.1)]

1 INDICATIONS AND USAGE

1.1 Schizophrenia

INVEGA (paliperidone) Extended-Release Tablets are indicated for the treatment of schizophrenia [see Clinical Studies (14.1)] .

The efficacy of INVEGA in schizophrenia was established in three 6-week trials in adults and one 6-week trial in adolescents, as well as one maintenance trial in adults.

1.2 Schizoaffective Disorder

INVEGA (paliperidone) Extended-Release Tablets are indicated for the treatment of schizoaffective disorder as monotherapy and an adjunct to mood stabilizers and/or antidepressant therapy [see Clinical Studies (14.2)] .

The efficacy of INVEGA in schizoaffective disorder was established in two 6-week trials in adults.

2 DOSAGE AND ADMINISTRATION

2.1 Schizophrenia

Adults

The recommended dose of INVEGA (paliperidone) Extended-Release Tablets for the treatment of schizophrenia in adults is 6 mg administered once daily. Initial dose titration is not required. Although it has not been systematically established that doses above 6 mg have additional benefit, there was a general trend for greater effects with higher doses. This must be weighed against the dose-related increase in adverse reactions. Thus, some patients may benefit from higher doses, up to 12 mg/day, and for some patients, a lower dose of 3 mg/day may be sufficient. Dose increases above 6 mg/day should be made only after clinical reassessment and generally should occur at intervals of more than 5 days. When dose increases are indicated, increments of 3 mg/day are recommended. The maximum recommended dose is 12 mg/day.

In a longer-term study, INVEGA has been shown to be effective in delaying time to relapse in patients with schizophrenia who were stabilized on INVEGA for 6 weeks [see Clinical Studies (14)] . INVEGA should be prescribed at the lowest effective dose for maintaining clinical stability and the physician should periodically reevaluate the long-term usefulness of the drug in individual patients.

Adolescents (12–17 years of age)

The recommended starting dose of INVEGA (paliperidone) Extended-Release Tablets for the treatment of schizophrenia in adolescents 12–17 years of age is 3 mg administered once daily. Initial dose titration is not required. Dose increases, if considered necessary, should be made only after clinical reassessment and should occur at increments of 3 mg/day at intervals of more than 5 days. Prescribers should be mindful that, in the adolescent schizophrenia study, there was no clear enhancement to efficacy at the higher doses, i.e., 6 mg for subjects weighing less than 51 kg and 12 mg for subjects weighing 51 kg or greater, while adverse events were dose-related.

2.2 Schizoaffective Disorder

The recommended dose of INVEGA (paliperidone) Extended-Release Tablets for the treatment of schizoaffective disorder in adults is 6 mg administered once daily. Initial dose titration is not required. Some patients may benefit from lower or higher doses within the recommended dose range of 3 to 12 mg once daily. A general trend for greater effects was seen with higher doses. This trend must be weighed against dose-related increase in adverse reactions. Dosage adjustment, if indicated, should occur only after clinical reassessment. Dose increases, if indicated, generally should occur at intervals of more than 4 days. When dose increases are indicated, increments of 3 mg/day are recommended. The maximum recommended dose is 12 mg/day.

2.3 Administration Instructions

INVEGA can be taken with or without food.

INVEGA must be swallowed whole with the aid of liquids. Tablets should not be chewed, divided, or crushed. The medication is contained within a nonabsorbable shell designed to release the drug at a controlled rate. The tablet shell, along with insoluble core components, is eliminated from the body; patients should not be concerned if they occasionally notice in their stool something that looks like a tablet.

2.4 Use with Risperidone

Concomitant use of INVEGA with risperidone has not been studied. Since paliperidone is the major active metabolite of risperidone, consideration should be given to the additive paliperidone exposure if risperidone is coadministered with INVEGA.

2.5 Dosage in Special Populations

Renal Impairment

Dosing must be individualized according to the patient's renal function status. For patients with mild renal impairment (creatinine clearance ≥ 50 mL/min to < 80 mL/min), the recommended initial dose of INVEGA is 3 mg once daily. The dose may then be increased to a maximum of 6 mg once daily based on clinical response and tolerability. For patients with moderate to severe renal impairment (creatinine clearance ≥ 10 mL/min to < 50 mL/min), the recommended initial dose of INVEGA is 3 mg every other day, which may be increased to a maximum of 3 mg once daily after clinical reassessment. As INVEGA has not been studied in patients with creatinine clearance below 10 mL/min, use is not recommended in such patients. [See Clinical Pharmacology (12.3)]

Hepatic Impairment

For patients with mild to moderate hepatic impairment, (Child-Pugh Classification A and B), no dose adjustment is recommended [see Clinical Pharmacology (12.3)] . INVEGA has not been studied in patients with severe hepatic impairment.

Elderly

Because elderly patients may have diminished renal function, dose adjustments may be required according to their renal function status. In general, recommended dosing for elderly patients with normal renal function is the same as for younger adult patients with normal renal function. For patients with moderate to severe renal impairment (creatinine clearance 10 mL/min to < 50 mL/min), the maximum recommended dose of INVEGA is 3 mg once daily [see Renal Impairment above] .

3 DOSAGE FORMS AND STRENGTHS

INVEGA Extended-Release Tablets are available in the following strengths and colors: 3 mg (white), 6 mg (beige), and 9 mg (pink). All tablets are capsule shaped and are imprinted with either "PAL 3", "PAL 6", or "PAL 9".

4 CONTRAINDICATIONS

INVEGA is contraindicated in patients with a known hypersensitivity to either paliperidone or risperidone, or to any of the excipients in the INVEGA formulation. Hypersensitivity reactions, including anaphylactic reactions and angioedema, have been reported in patients treated with risperidone and in patients treated with paliperidone. Paliperidone is a metabolite of risperidone.

5 WARNINGS AND PRECAUTIONS

5.1 Increased Mortality in Elderly Patients with Dementia-Related Psychosis

Elderly patients with dementia-related psychosis treated with antipsychotic drugs are at an increased risk of death. Analyses of 17 placebo-controlled trials (modal duration of 10 weeks), largely in patients taking atypical antipsychotic drugs, revealed a risk of death in drug-treated patients of between 1.6 to 1.7 times the risk of death in placebo-treated patients. Over the course of a typical 10-week controlled trial, the rate of death in drug-treated patients was about 4.5%, compared to a rate of about 2.6% in the placebo group. Although the causes of death were varied, most of the deaths appeared to be either cardiovascular (e.g., heart failure, sudden death) or infectious (e.g., pneumonia) in nature. Observational studies suggest that, similar to atypical antipsychotic drugs, treatment with conventional antipsychotic drugs may increase mortality. The extent to which the findings of increased mortality in observational studies may be attributed to the antipsychotic drug as opposed to some characteristic(s) of the patients is not clear. INVEGA (paliperidone) is not approved for the treatment of dementia-related psychosis [see Boxed Warning] .

5.2 Cerebrovascular Adverse Reactions, Including Stroke, in Elderly Patients with Dementia-Related Psychosis

In placebo-controlled trials with risperidone, aripiprazole, and olanzapine in elderly subjects with dementia, there was a higher incidence of cerebrovascular adverse reactions (cerebrovascular accidents and transient ischemic attacks) including fatalities compared to placebo-treated subjects. INVEGA was not marketed at the time these studies were performed. INVEGA is not approved for the treatment of patients with dementia-related psychosis [see also Boxed Warning and Warnings and Precautions (5.1)] .

5.3 Neuroleptic Malignant Syndrome

Neuroleptic Malignant Syndrome (NMS), a potentially fatal symptom complex, has been reported in association with antipsychotic drugs, including paliperidone. Clinical manifestations of NMS are hyperpyrexia, muscle rigidity, altered mental status including delirium, and autonomic instability (irregular pulse or blood pressure, tachycardia, diaphoresis, and cardiac dysrhythmia). Additional signs may include elevated creatine phosphokinase, myoglobinuria, rhabdomyolysis, and acute renal failure.

If NMS is suspected, immediately discontinue INVEGA and provide symptomatic treatment and monitoring.

5.4 QT Prolongation

Paliperidone causes a modest increase in the corrected QT (QTc) interval. The use of paliperidone should be avoided in combination with other drugs that are known to prolong QTc including Class 1A (e.g., quinidine, procainamide) or Class III (e.g., amiodarone, sotalol) antiarrhythmic medications, antipsychotic medications (e.g., chlorpromazine, thioridazine), antibiotics (e.g., gatifloxacin, moxifloxacin), or any other class of medications known to prolong the QTc interval. Paliperidone should also be avoided in patients with congenital long QT syndrome and in patients with a history of cardiac arrhythmias.

Certain circumstances may increase the risk of the occurrence of torsade de pointes and/or sudden death in association with the use of drugs that prolong the QTc interval, including (1) bradycardia; (2) hypokalemia or hypomagnesemia; (3) concomitant use of other drugs that prolong the QTc interval; and (4) presence of congenital prolongation of the QT interval.

The effects of paliperidone on the QT interval were evaluated in a double-blind, active-controlled (moxifloxacin 400 mg single dose), multicenter QT study in adults with schizophrenia and schizoaffective disorder, and in three placebo- and active-controlled 6-week, fixed-dose efficacy trials in adults with schizophrenia.

In the QT study (n=141), the 8 mg dose of immediate-release oral paliperidone (n=50) showed a mean placebo-subtracted increase from baseline in QTcLD of 12.3 msec (90% CI: 8.9; 15.6) on day 8 at 1.5 hours post-dose. The mean steady-state peak plasma concentration for this 8 mg dose of paliperidone immediate-release was more than twice the exposure observed with the maximum recommended 12 mg dose of INVEGA (Cmax ss = 113 ng/mL and 45 ng/mL, respectively, when administered with a standard breakfast). In this same study, a 4 mg dose of the immediate-release oral formulation of paliperidone, for which Cmax ss = 35 ng/mL, showed an increased placebo-subtracted QTcLD of 6.8 msec (90% CI: 3.6; 10.1) on day 2 at 1.5 hours post-dose. None of the subjects had a change exceeding 60 msec or a QTcLD exceeding 500 msec at any time during this study.

For the three fixed-dose efficacy studies in subjects with schizophrenia, electrocardiogram (ECG) measurements taken at various time points showed only one subject in the INVEGA 12 mg group had a change exceeding 60 msec at one time-point on Day 6 (increase of 62 msec). No subject receiving INVEGA had a QTcLD exceeding 500 msec at any time in any of these three studies.

5.5 Tardive Dyskinesia

Tardive dyskinesia, a syndrome consisting of potentially irreversible, involuntary, dyskinetic movements, may develop in patients treated with antipsychotic drugs. Although the prevalence of the syndrome appears to be highest among the elderly, especially elderly women, it is impossible to predict which patients will develop the syndrome. Whether antipsychotic drug products differ in their potential to cause tardive dyskinesia is unknown.

The risk of developing tardive dyskinesia and the likelihood that it will become irreversible appear to increase with duration of treatment and the cumulative dose. The syndrome can develop after relatively brief treatment periods, even at low doses. It may also occur after discontinuation of treatment.

Tardive dyskinesia may remit, partially or completely, if antipsychotic treatment is withdrawn. Antipsychotic treatment, itself, however, may suppress (or partially suppress) the signs and symptoms of the syndrome and thereby may possibly mask the underlying process. The effect that symptomatic suppression has upon the long-term course of the syndrome is unknown.

Given these considerations, INVEGA should be prescribed in a manner that is most likely to minimize the occurrence of tardive dyskinesia. Chronic antipsychotic treatment should generally be reserved for patients: (1) who suffer from a chronic illness that is known to respond to antipsychotic drugs, and (2) for whom alternative, equally effective, but potentially less harmful treatments are not available or appropriate. In patients who do require chronic treatment, use the lowest dose and the shortest duration of treatment producing a satisfactory clinical response. Periodically reassess the need for continued treatment.

If signs and symptoms of tardive dyskinesia appear in a patient on INVEGA, drug discontinuation should be considered. However, some patients may require treatment with INVEGA despite the presence of the syndrome.

5.6 Metabolic Changes

Atypical antipsychotic drugs have been associated with metabolic changes that may increase cardiovascular/cerebrovascular risk. These metabolic changes include hyperglycemia, dyslipidemia, and body weight gain. While all of the drugs in the class have been shown to produce some metabolic changes, each drug has its own specific risk profile.

Hyperglycemia and Diabetes Mellitus

Hyperglycemia and diabetes mellitus, in some cases extreme and associated with ketoacidosis or hyperosmolar coma or death, have been reported in patients treated with all atypical antipsychotics. These cases were, for the most part, seen in postmarketing clinical use and epidemiologic studies, not in clinical trials, and there have been few reports of hyperglycemia or diabetes in trial subjects treated with INVEGA. Assessment of the relationship between atypical antipsychotic use and glucose abnormalities is complicated by the possibility of an increased background risk of diabetes mellitus in patients with schizophrenia and the increasing incidence of diabetes mellitus in the general population. Given these confounders, the relationship between atypical antipsychotic use and hyperglycemia-related adverse events is not completely understood. However, epidemiological studies suggest an increased risk of treatment-emergent hyperglycemia-related adverse events in patients treated with the atypical antipsychotics. Because INVEGA was not marketed at the time these studies were performed, it is not known if INVEGA is associated with this increased risk.

Patients with an established diagnosis of diabetes mellitus who are started on atypical antipsychotics should be monitored regularly for worsening of glucose control. Patients with risk factors for diabetes mellitus (e.g., obesity, family history of diabetes) who are starting treatment with atypical antipsychotics should undergo fasting blood glucose testing at the beginning of treatment and periodically during treatment. Any patient treated with atypical antipsychotics should be monitored for symptoms of hyperglycemia including polydipsia, polyuria, polyphagia, and weakness. Patients who develop symptoms of hyperglycemia during treatment with atypical antipsychotics should undergo fasting blood glucose testing. In some cases, hyperglycemia has resolved when the atypical antipsychotic was discontinued; however, some patients required continuation of anti-diabetic treatment despite discontinuation of the suspect drug.

Pooled data from the three placebo-controlled, 6-week, fixed-dose studies in adult subjects with schizophrenia are presented in Table 1a.

Table 1a. Change in Fasting Glucose from Three Placebo-Controlled, 6-Week, Fixed-Dose Studies in Adult Subjects with Schizophrenia
 |  |  | INVEGA
 | Placebo | 3 mg/day | 6 mg/day | 9 mg/day | 12 mg/day
 | Mean change from baseline (mg/dL)
 | n=322 | n=122 | n=212 | n=234 | n=218
Serum Glucose Change from baseline | 0.8 | -0.7 | 0.4 | 2.3 | 4.3
 | Proportion of Patients with Shifts
Serum Glucose Normal to High | 5.1% | 3.2% | 4.5% | 4.8% | 3.8%
(<100 mg/dL to ≥126 mg/dL) | (12/236) | (3/93) | (7/156) | (9/187) | (6/157)

In the uncontrolled, longer-term open-label extension studies, INVEGA was associated with a mean change in glucose of +3.3 mg/dL at Week 24 (n=570) and +4.6 mg/dL at Week 52 (n=314).

Data from the placebo-controlled 6-week study in adolescent subjects (12–17 years of age) with schizophrenia are presented in Table 1b.

Table 1b. Change in Fasting Glucose from a Placebo-Controlled 6-Week Study in Adolescent Subjects (12–17 years of age) with Schizophrenia
 |  | INVEGA
 | Placebo | 1.5 mg/day | 3 mg/day | 6 mg/day | 12 mg/day
 | Mean change from baseline (mg/dL)
 | n=41 | n=44 | n=11 | n=28 | n=32
Serum Glucose Change from baseline | 0.8 | -1.4 | -1.8 | -0.1 | 5.2
 | Proportion of Patients with Shifts
Serum Glucose Normal to High | 3% | 0% | 0% | 0% | 11%
(<100 mg/dL to ≥126 mg/dL) | (1/32) | (0/34) | (0/9) | (0/20) | (3/27)

Dyslipidemia

Undesirable alterations in lipids have been observed in patients treated with atypical antipsychotics.

Pooled data from the three placebo-controlled, 6-week, fixed-dose studies in adult subjects with schizophrenia are presented in Table 2a.

Table 2a. Change in Fasting Lipids from Three Placebo-Controlled, 6-Week, Fixed-Dose Studies in Adult Subjects with Schizophrenia
 |  | INVEGA
 | Placebo | 3 mg/day | 6 mg/day | 9 mg/day | 12 mg/day
 | Mean change from baseline (mg/dL)
Cholesterol | n=331 | n=120 | n=216 | n=236 | n=231
Change from baseline | -6.3 | -4.4 | -2.4 | -5.3 | -4.0
LDL | n=322 | n=116 | n=210 | n=231 | n=225
Change from baseline | -3.2 | 0.5 | -0.8 | -3.9 | -2.0
HDL | n=331 | n=119 | n=216 | n=234 | n=230
Change from baseline | 0.3 | -0.4 | 0.5 | 0.8 | 1.2
Triglycerides | n=331 | n=120 | n=216 | n=236 | n=231
Change from baseline | -22.3 | -18.3 | -12.6 | -10.6 | -15.4
 | Proportion of Patients with Shifts
Cholesterol
Normal to High | 2.6% | 2.8% | 5.6% | 4.1% | 3.1%
(<200 mg/dL to ≥240 mg/dL) | (5/194) | (2/71) | (7/125) | (6/147) | (4/130)
LDL
Normal to High | 1.9% | 0.0% | 5.0% | 3.7% | 0.0%
(<100 mg/dL to ≥160 mg/dL) | (2/105) | (0/44) | (3/60) | (3/81) | (0/69)
HDL
Normal to Low | 22.0% | 16.3% | 29.1% | 23.4% | 20.0%
(≥40 mg/dL to <40 mg/dL) | (44/200) | (13/80) | (39/134) | (32/137) | (27/135)
Triglycerides
Normal to High | 5.3% | 11.0% | 8.8% | 8.7% | 4.3%
(<150 mg/dL to ≥200 mg/dL) | (11/208) | (9/82) | (12/136) | (13/150) | (6/139)

In the uncontrolled, longer-term open-label extension studies, INVEGA was associated with a mean change in (a) total cholesterol of -1.5 mg/dL at Week 24 (n=573) and -1.5 mg/dL at Week 52 (n=317), (b) triglycerides of -6.4 mg/dL at Week 24 (n=573) and -10.5 mg/dL at Week 52 (n=317); (c) LDL of -1.9 mg/dL at Week 24 (n=557) and -2.7 mg/dL at Week 52 (n=297); and (d) HDL of +2.2 mg/dL at Week 24 (n=568) and +3.6 mg/dL at Week 52 (n=302).

Data from the placebo-controlled 6-week study in adolescent subjects (12–17 years of age) with schizophrenia are presented in Table 2b.

Table 2b. Change in Fasting Lipids from a Placebo-Controlled 6-Week Study in Adolescent Subjects (12–17 years of age) with Schizophrenia
 |  | INVEGA
 | Placebo | 1.5 mg/day | 3 mg/day | 6 mg/day | 12 mg/day
 | Mean change from baseline (mg/dL)
Cholesterol | n=39 | n=45 | n=11 | n=28 | n=32
Change from baseline | -7.8 | -3.3 | 12.7 | 3.0 | -1.5
LDL | n=37 | n=40 | n=9 | n=27 | n=31
Change from baseline | -4.1 | -3.1 | 7.2 | 2.4 | 0.6
HDL | n=37 | n=41 | n=9 | n=27 | n=31
Change from baseline | -1.9 | 0.0 | 1.3 | 1.4 | 0.0
Triglycerides | n=39 | n=44 | n=11 | n=28 | n=32
Change from baseline | -8.9 | 3.2 | 17.6 | -5.4 | 3.9
 | Proportion of Patients with Shifts
Cholesterol
Normal to High | 7% | 4% | 0% | 6% | 11%
(<170 mg/dL to ≥200 mg/dL) | (2/27) | (1/26) | (0/6) | (1/18) | (2/19)
LDL
Normal to High | 3% | 4% | 14% | 0% | 9%
(<110 mg/dL to ≥130 mg/dL) | (1/32) | (1/25) | (1/7) | (0/22) | (2/22)
HDL
Normal to Low | 14% | 7% | 29% | 13% | 23%
(≥40 mg/dL to <40 mg/dL) | (4/28) | (2/30) | (2/7) | (3/23) | (5/22)
Triglycerides
Normal to High | 3% | 5% | 13% | 8% | 7%
(<150 mg/dL to ≥200 mg/dL) | (1/34) | (2/38) | (1/8) | (2/26) | (2/28)

Weight Gain

Weight gain has been observed with atypical antipsychotic use. Clinical monitoring of weight is recommended.

Schizophrenia Trials

Data on mean changes in body weight and the proportion of subjects meeting a weight gain criterion of ≥ 7% of body weight from the three placebo-controlled, 6-week, fixed-dose studies in adult subjects are presented in Table 3a.

Table 3a. Mean Change in Body Weight (kg) and the Proportion of Subjects with ≥ 7% Gain in Body Weight from Three Placebo-Controlled, 6-Week, Fixed-Dose Studies in Adult Subjects with Schizophrenia
 |  | INVEGA
 | Placebo | 3 mg/day | 6 mg/day | 9 mg/day | 12 mg/day
 | n=323 | n=112 | n=215 | n=235 | n=218
Weight (kg) Change from baseline | -0.4 | 0.6 | 0.6 | 1.0 | 1.1
Weight Gain ≥ 7% increase from baseline | 5% | 7% | 6% | 9% | 9%

In the uncontrolled, longer-term open-label extension studies, INVEGA was associated with a mean change in weight of +1.4 kg at Week 24 (n=63) and +2.6 kg at Week 52 (n=302).

Weight gain in adolescent subjects with schizophrenia was assessed in a 6-week, double-blind, placebo-controlled study and an open-label extension with a median duration of exposure to INVEGA of 182 days. Data on mean changes in body weight and the proportion of subjects meeting a weight gain criterion of ≥ 7% of body weight [see Clinical Studies (14.1)] from the placebo-controlled 6-week study in adolescent subjects (12–17 years of age) are presented in Table 3b.

Table 3b. Mean Change in Body Weight (kg) and the Proportion of Subjects with ≥ 7% Gain in Body Weight from a Placebo-Controlled 6-Week Study in Adolescent Subjects (12–17 years of age) with Schizophrenia
 |  | INVEGA
 | Placebo | 1.5 mg/day | 3 mg/day | 6 mg/day | 12 mg/day
 | n=51 | n=54 | n=16 | n=45 | n=34
Weight (kg) Change from baseline | 0.0 | 0.3 | 0.8 | 1.2 | 1.5
Weight Gain ≥ 7% increase from baseline | 2% | 6% | 19% | 7% | 18%

In the open-label long-term study the proportion of total subjects treated with INVEGA with an increase in body weight of ≥ 7% from baseline was 33%. When treating adolescent patients with INVEGA, weight gain should be assessed against that expected with normal growth. When taking into consideration the median duration of exposure to INVEGA in the open-label study (182 days) along with expected normal growth in this population based on age and gender, an assessment of standardized scores relative to normative data provides a more clinically relevant measure of changes in weight. The mean change from open-label baseline to endpoint in standardized score for weight was 0.1 (4% above the median for normative data). Based on comparison to the normative data, these changes are not considered to be clinically significant.

Schizoaffective Disorder Trials

In the pooled data from the two placebo-controlled, 6-week studies in adult subjects with schizoaffective disorder, a higher percentage of INVEGA-treated subjects (5%) had an increase in body weight of ≥ 7% compared with placebo-treated subjects (1%). In the study that examined high- and low-dose groups, the increase in body weight of ≥ 7% was 3% in the low-dose group, 7% in the high-dose group, and 1% in the placebo group.

5.7 Hyperprolactinemia

Like other drugs that antagonize dopamine D2 receptors, paliperidone elevates prolactin levels and the elevation persists during chronic administration. Paliperidone has a prolactin-elevating effect similar to that seen with risperidone, a drug that is associated with higher levels of prolactin than other antipsychotic drugs.

Hyperprolactinemia, regardless of etiology, may suppress hypothalamic GnRH, resulting in reduced pituitary gonadotrophin secretion. This, in turn, may inhibit reproductive function by impairing gonadal steroidogenesis in both female and male patients. Galactorrhea, amenorrhea, gynecomastia, and impotence have been reported in patients receiving prolactin-elevating compounds. Long-standing hyperprolactinemia when associated with hypogonadism may lead to decreased bone density in both female and male subjects.

Tissue culture experiments indicate that approximately one-third of human breast cancers are prolactin dependent in vitro, a factor of potential importance if the prescription of these drugs is considered in a patient with previously detected breast cancer. An increase in the incidence of pituitary gland, mammary gland, and pancreatic islet cell neoplasia (mammary adenocarcinomas, pituitary and pancreatic adenomas) was observed in the risperidone carcinogenicity studies conducted in mice and rats [see Nonclinical Toxicology (13.1)] . Published epidemiologic studies have shown inconsistent results when exploring the potential association between hyperprolactinemia and breast cancer.

5.8 Potential for Gastrointestinal Obstruction

Because the INVEGA tablet is non-deformable and does not appreciably change in shape in the gastrointestinal tract, INVEGA should ordinarily not be administered to patients with pre-existing severe gastrointestinal narrowing (pathologic or iatrogenic, for example: esophageal motility disorders, small bowel inflammatory disease, "short gut" syndrome due to adhesions or decreased transit time, past history of peritonitis, cystic fibrosis, chronic intestinal pseudo-obstruction, or Meckel's diverticulum). There have been rare reports of obstructive symptoms in patients with known strictures in association with the ingestion of drugs in non-deformable controlled-release formulations. Because of the controlled-release design of the tablet, INVEGA should only be used in patients who are able to swallow the tablet whole [see Dosage and Administration (2.3) and Patient Counseling Information (17)] .

A decrease in transit time, e.g., as seen with diarrhea, would be expected to decrease bioavailability and an increase in transit time, e.g., as seen with gastrointestinal neuropathy, diabetic gastroparesis, or other causes, would be expected to increase bioavailability. These changes in bioavailability are more likely when the changes in transit time occur in the upper GI tract.

5.9 Orthostatic Hypotension and Syncope

Paliperidone can induce orthostatic hypotension and syncope in some patients because of its alpha-blocking activity. In pooled results of the three placebo-controlled, 6-week, fixed-dose trials in subjects with schizophrenia, syncope was reported in 0.8% (7/850) of subjects treated with INVEGA (3 mg, 6 mg, 9 mg, 12 mg) compared to 0.3% (1/355) of subjects treated with placebo.

INVEGA should be used with caution in patients with known cardiovascular disease (e.g., heart failure, history of myocardial infarction or ischemia, conduction abnormalities), cerebrovascular disease, or conditions that predispose the patient to hypotension (e.g., dehydration, hypovolemia, and treatment with antihypertensive medications). Monitoring of orthostatic vital signs should be considered in patients who are vulnerable to hypotension.

5.10 Falls

Somnolence, postural hypotension, motor and sensory instability have been reported with the use of antipsychotics, including INVEGA, which may lead to falls and, consequently, fractures or other fall-related injuries. For patients, particularly the elderly, with diseases, conditions, or medications that could exacerbate these effects, assess the risk of falls when initiating antipsychotic treatment and recurrently for patients on long-term antipsychotic therapy.

5.11 Leukopenia, Neutropenia, and Agranulocytosis

In clinical trial and/or postmarketing experience, events of leukopenia/neutropenia have been reported temporally related to antipsychotic agents, including INVEGA. Agranulocytosis has also been reported.

Possible risk factors for leukopenia/neutropenia include pre-existing low white blood cell count (WBC)/absolute neutrophil count (ANC) and history of drug-induced leukopenia/neutropenia. In patients with a history of a clinically significant low WBC/ANC or a drug-induced leukopenia/neutropenia, perform a complete blood count (CBC) frequently during the first few months of therapy. In such patients, consider discontinuation of INVEGA at the first sign of a clinically significant decline in WBC in the absence of other causative factors.

Monitor patients with clinically significant neutropenia for fever or other symptoms or signs of infection and treat promptly if such symptoms or signs occur. Discontinue INVEGA in patients with severe neutropenia (absolute neutrophil count < 1000/mm^3) and follow their WBC until recovery.

5.12 Potential for Cognitive and Motor Impairment

Somnolence, sedation, and dizziness were reported as adverse reactions in subjects treated with INVEGA [see Adverse Reactions (6.2)] . Antipsychotics, including INVEGA, have the potential to impair judgment, thinking, or motor skills. Patients should be cautioned about performing activities requiring mental alertness, such as operating hazardous machinery or operating a motor vehicle, until they are reasonably certain that paliperidone therapy does not adversely affect them.

5.13 Seizures

During premarketing clinical trials in subjects with schizophrenia (the three placebo-controlled, 6-week, fixed-dose studies and a study conducted in elderly schizophrenic subjects), seizures occurred in 0.22% of subjects treated with INVEGA (3 mg, 6 mg, 9 mg, 12 mg) and 0.25% of subjects treated with placebo. Like other antipsychotic drugs, INVEGA should be used cautiously in patients with a history of seizures or other conditions that potentially lower the seizure threshold. Conditions that lower the seizure threshold may be more prevalent in patients 65 years or older.

5.14 Dysphagia

Esophageal dysmotility and aspiration have been associated with antipsychotic drug use. Aspiration pneumonia is a common cause of morbidity and mortality in patients with advanced Alzheimer's dementia. INVEGA and other antipsychotic drugs should be used cautiously in patients at risk for aspiration pneumonia.

5.15 Priapism

Drugs with alpha-adrenergic blocking effects have been reported to induce priapism. Priapism has been reported with INVEGA during postmarketing surveillance. Severe priapism may require surgical intervention.

5.16 Body Temperature Regulation

Disruption of the body's ability to reduce core body temperature has been attributed to antipsychotic agents. Appropriate care is advised when prescribing INVEGA to patients who will be experiencing conditions which may contribute to an elevation in core body temperature, e.g., exercising strenuously, exposure to extreme heat, receiving concomitant medication with anticholinergic activity, or being subject to dehydration.

6 ADVERSE REACTIONS

The following adverse reactions are discussed in more detail in other sections of the labeling:

- Increased mortality in elderly patients with dementia-related psychosis [see Boxed Warning and Warnings and Precautions (5.1)]
- Cerebrovascular adverse reactions, including stroke, in elderly patients with dementia-related psychosis [see Warnings and Precautions (5.2)]
- Neuroleptic malignant syndrome [see Warnings and Precautions (5.3)]
- QT prolongation [see Warnings and Precautions (5.4)]
- Tardive dyskinesia [see Warnings and Precautions (5.5)]
- Metabolic changes [see Warnings and Precautions (5.6)]
- Hyperprolactinemia [see Warnings and Precautions (5.7)]
- Potential for gastrointestinal obstruction [see Warnings and Precautions (5.8)]
- Orthostatic hypotension and syncope [see Warnings and Precautions (5.9)]
- Falls [see Warnings and Precautions (5.10)]
- Leukopenia, neutropenia, and agranulocytosis [see Warnings and Precautions (5.11)]
- Potential for cognitive and motor impairment [see Warnings and Precautions (5.12)]
- Seizures [see Warnings and Precautions (5.13)]
- Dysphagia [see Warnings and Precautions (5.14)]
- Priapism [see Warnings and Precautions (5.15)]
- Disruption of body temperature regulation [see Warnings and Precautions (5.16)]

6.1 Clinical Trials Experience

The most common adverse reactions in clinical trials in adult subjects with schizophrenia (reported in 5% or more of subjects treated with INVEGA and at least twice the placebo rate in any of the dose groups) were extrapyramidal symptoms, tachycardia, and akathisia. The most common adverse reactions in clinical trials in adult patients with schizoaffective disorder (reported in 5% or more of subjects treated with INVEGA and at least twice the placebo rate) were extrapyramidal symptoms, somnolence, dyspepsia, constipation, weight increased, and nasopharyngitis.

The most common adverse reactions that were associated with discontinuation from clinical trials in adult subjects with schizophrenia (causing discontinuation in 2% of INVEGA-treated subjects) were nervous system disorders. The most common adverse reactions that were associated with discontinuation from clinical trials in adult subjects with schizoaffective disorder were gastrointestinal disorders, which resulted in discontinuation in 1% of INVEGA-treated subjects. [See Adverse Reactions (6)] .

The safety of INVEGA was evaluated in 1205 adult subjects with schizophrenia who participated in three placebo-controlled, 6-week, double-blind trials, of whom 850 subjects received INVEGA at fixed doses ranging from 3 mg to 12 mg once daily. The information presented in this section was derived from pooled data from these three trials. Additional safety information from the placebo-controlled phase of the long-term maintenance study, in which subjects received INVEGA at daily doses within the range of 3 mg to 15 mg (n=104), is also included.

The safety of INVEGA was evaluated in 150 adolescent subjects 12–17 years of age with schizophrenia who received INVEGA in the dose range of 1.5 mg to 12 mg/day in a 6-week, double-blind, placebo-controlled trial.

The safety of INVEGA was also evaluated in 622 adult subjects with schizoaffective disorder who participated in two placebo-controlled, 6-week, double-blind trials. In one of these trials, 206 subjects were assigned to one of two dose levels of INVEGA: 6 mg with the option to reduce to 3 mg (n=108) or 12 mg with the option to reduce to 9 mg (n=98) once daily. In the other study, 214 subjects received flexible doses of INVEGA (3–12 mg once daily). Both studies included subjects who received INVEGA either as monotherapy or as an adjunct to mood stabilizers and/or antidepressants. Adverse events during exposure to study treatment were obtained by general inquiry and recorded by clinical investigators using their own terminology. Consequently, to provide a meaningful estimate of the proportion of individuals experiencing adverse events, events were grouped in standardized categories using MedDRA terminology.

Throughout this section, adverse reactions are reported. Adverse reactions are adverse events that were considered to be reasonably associated with the use of INVEGA (adverse drug reactions) based on the comprehensive assessment of the available adverse event information. A causal association for INVEGA often cannot be reliably established in individual cases. Further, because clinical trials are conducted under widely varying conditions, adverse reaction rates observed in the clinical trials of a drug cannot be directly compared to rates in the clinical trials of another drug and may not reflect the rates observed in clinical practice.

Commonly-Observed Adverse Reactions in Double-Blind, Placebo-Controlled Clinical Trials – Schizophrenia in Adults and Adolescents

Adult Patients with Schizophrenia

Table 4 enumerates the pooled incidences of adverse reactions reported in the three placebo-controlled, 6-week, fixed-dose studies in adults, listing those that occurred in 2% or more of subjects treated with INVEGA in any of the dose groups, and for which the incidence in INVEGA-treated subjects in any of the dose groups was greater than the incidence in subjects treated with placebo.

Table 4. Adverse Reactions Reported by ≥ 2% of INVEGA-Treated Adult Subjects with Schizophrenia in Three Short-Term, Fixed-Dose, Placebo-Controlled Clinical Trials [Table includes adverse reactions that were reported in 2% or more of subjects in any of the INVEGA dose groups and which occurred at greater incidence than in the placebo group. Data are pooled from three studies; one study included once-daily INVEGA doses of 3 mg and 9 mg, the second study included 6 mg, 9 mg, and 12 mg, and the third study included 6 mg and 12 mg [see Clinical Studies (14)] . Extrapyramidal symptoms includes the terms dyskinesia, dystonia, extrapyramidal disorder, hypertonia, muscle rigidity, oculogyration, parkinsonism, and tremor. Somnolence includes the terms sedation and somnolence. Tachycardia includes the terms tachycardia, sinus tachycardia, and heart rate increased. Adverse reactions for which the INVEGA incidence was equal to or less than placebo are not listed in the table, but included the following: vomiting.]
 | Percentage of Patients
 |  | INVEGA
 | Placebo | 3 mg once daily | 6 mg once daily | 9 mg once daily | 12 mg once daily
Body System or Organ Class | (N=355) | (N=127) | (N=235) | (N=246) | (N=242)
Dictionary-Derived Term
Total percentage of subjects with adverse reactions | 37 | 48 | 47 | 53 | 59
Cardiac disorders
Atrioventricular block first degree | 1 | 2 | 0 | 2 | 1
Bundle branch block | 2 | 3 | 1 | 3 | <1
Sinus arrhythmia | 0 | 2 | 1 | 1 | <1
Tachycardia | 7 | 14 | 12 | 12 | 14
Gastrointestinal disorders
Abdominal pain upper | 1 | 1 | 3 | 2 | 2
Dry mouth | 1 | 2 | 3 | 1 | 3
Salivary hypersecretion | <1 | 0 | <1 | 1 | 4
General disorders
Asthenia | 1 | 2 | <1 | 2 | 2
Fatigue | 1 | 2 | 1 | 2 | 2
Nervous system disorders
Akathisia | 4 | 4 | 3 | 8 | 10
Dizziness | 4 | 6 | 5 | 4 | 5
Extrapyramidal symptoms | 8 | 10 | 7 | 20 | 18
Headache | 12 | 11 | 12 | 14 | 14
Somnolence | 7 | 6 | 9 | 10 | 11
Vascular disorders
Orthostatic hypotension | 1 | 2 | 1 | 2 | 4

Adolescent Patients with Schizophrenia

Table 5 lists the adverse reactions reported in a fixed-dose, placebo-controlled study in adolescent subjects 12–17 years of age with schizophrenia, listing those that occurred in 2% or more of subjects treated with INVEGA in any of the dose groups, and for which the incidence in INVEGA-treated subjects in any of the dose groups was greater than the incidence in subjects treated with placebo.

Table 5. Adverse Reactions Reported by ≥ 2% of INVEGA-Treated Adolescent Subjects with Schizophrenia in a Fixed-Dose, Placebo-Controlled Clinical Trial [Table includes adverse reactions that were reported in 2% or more of subjects in any of the INVEGA dose groups and which occurred at greater incidence than in the placebo group. Extrapyramidal symptoms includes the terms oculogyric crisis, muscle rigidity, musculoskeletal stiffness, nuchal rigidity, torticollis, trismus, bradykinesia, cogwheel rigidity, dyskinesia, dystonia, extrapyramidal disorder, hypertonia, hypokinesia, muscle contractions involuntary, parkinsonian gait, parkinsonism, tremor, and restlessness. Somnolence includes the terms somnolence, sedation, and hypersomnia. Insomnia includes the terms insomnia and initial insomnia. Tachycardia includes the terms tachycardia, sinus tachycardia, and heart rate increased. Hypertension includes the terms hypertension and blood pressure increased. Gynecomastia includes the terms gynecomastia and breast swelling.]
 | Percentage of Patients
 |  | INVEGA
 | Placebo | 1.5 mg once daily | 3 mg once daily | 6 mg once daily | 12 mg once daily
Body System or Organ Class | (N=51) | (N=54) | (N=16) | (N=45) | (N=35)
Dictionary-Derived Term
Total percentage of subjects with adverse reactions | 43 | 37 | 50 | 58 | 74
Cardiac disorders
Tachycardia | 0 | 0 | 6 | 9 | 6
Eye disorders
Vision blurred | 0 | 0 | 0 | 0 | 3
Gastrointestinal disorders
Dry mouth | 2 | 0 | 0 | 0 | 3
Salivary hypersecretion | 0 | 2 | 6 | 2 | 0
Swollen tongue | 0 | 0 | 0 | 0 | 3
Vomiting | 10 | 0 | 6 | 11 | 3
General disorders
Asthenia | 0 | 0 | 0 | 2 | 3
Fatigue | 0 | 4 | 0 | 2 | 3
Infections and infestations
Nasopharyngitis | 2 | 4 | 0 | 4 | 0
Investigations
Weight increased | 0 | 7 | 6 | 2 | 3
Nervous system disorders
Akathisia | 0 | 4 | 6 | 11 | 17
Dizziness | 0 | 2 | 6 | 2 | 3
Extrapyramidal symptoms | 0 | 4 | 19 | 18 | 23
Headache | 4 | 9 | 6 | 4 | 14
Lethargy | 0 | 0 | 0 | 0 | 3
Somnolence | 4 | 9 | 13 | 20 | 26
Tongue paralysis | 0 | 0 | 0 | 0 | 3
Psychiatric disorders
Anxiety | 4 | 0 | 0 | 2 | 9
Reproductive system and breast disorders
Amenorrhea | 0 | 0 | 6 | 0 | 0
Galactorrhea | 0 | 0 | 0 | 4 | 0
Gynecomastia | 0 | 0 | 0 | 0 | 3
Respiratory, thoracic and mediastinal disorders
Epistaxis | 0 | 0 | 0 | 2 | 0

Commonly-Observed Adverse Reactions in Double-Blind, Placebo-Controlled Clinical Trials – Schizoaffective Disorder in Adults

Table 6 enumerates the pooled incidences of adverse reactions reported in the two placebo-controlled 6-week studies in adult subjects, listing those that occurred in 2% or more of subjects treated with INVEGA and for which the incidence in INVEGA -treated subjects was greater than the incidence in subjects treated with placebo.

Table 6. Adverse Drug Reactions Reported by ≥ 2% of INVEGA -Treated Adult Subjects with Schizoaffective Disorder in Two Double-Blind, Placebo-Controlled Clinical Trials [Table includes adverse reactions that were reported in 2% or more of subjects in any of the INVEGA dose groups and which occurred at greater incidence than in the placebo group. Data are pooled from two studies. One study included once-daily INVEGA doses of 6 mg (with the option to reduce to 3 mg) and 12 mg (with the option to reduce to 9 mg). The second study included flexible once-daily doses of 3 to 12 mg. Among the 420 subjects treated with INVEGA, 230 (55%) received INVEGA as monotherapy and 190 (45%) received INVEGA as an adjunct to mood stabilizers and/or antidepressants. Extrapyramidal symptoms includes the terms bradykinesia, drooling, dyskinesia, dystonia, hypertonia, muscle rigidity, muscle twitching, oculogyration, parkinsonian gait, parkinsonism, restlessness, and tremor. Somnolence includes the terms sedation and somnolence. Tachycardia includes the terms tachycardia, sinus tachycardia, and heart rate increased.]
 | Percentage of Patients
 |  | INVEGA | INVEGA | INVEGA
 | Placebo | 3–6 mg once-daily fixed-dose range | 9–12 mg once-daily fixed-dose range | 3–12 mg once-daily flexible dose
Body System or Organ Class | (N=202) | (N=108) | (N=98) | (N=214)
Dictionary-Derived Term
Total percentage of subjects with adverse reactions | 32 | 48 | 50 | 43
Cardiac disorders
Tachycardia | 2 | 3 | 1 | 2
Gastrointestinal disorders
Abdominal discomfort/Abdominal pain upper | 1 | 1 | 0 | 3
Constipation | 2 | 4 | 5 | 4
Dyspepsia | 2 | 5 | 6 | 6
Nausea | 6 | 8 | 8 | 5
Stomach discomfort | 1 | 0 | 1 | 2
General disorders
Asthenia | 1 | 3 | 4 | <1
Infections and Infestations
Nasopharyngitis | 1 | 2 | 5 | 3
Rhinitis | 0 | 1 | 3 | 1
Upper respiratory tract infection | 1 | 2 | 2 | 2
Investigations
Weight increased | 1 | 5 | 4 | 4
Metabolism and nutrition disorders
Decreased appetite | <1 | 1 | 0 | 2
Increased appetite | <1 | 3 | 2 | 2
Musculoskeletal and connective tissue disorders
Back pain | 1 | 1 | 1 | 3
Myalgia | <1 | 2 | 4 | 1
Nervous system disorders
Akathisia | 4 | 4 | 6 | 6
Dysarthria | 0 | 1 | 4 | 2
Extrapyramidal symptoms | 8 | 20 | 17 | 12
Somnolence | 5 | 12 | 12 | 8
Psychiatric disorders
Sleep disorder | <1 | 2 | 3 | 0
Respiratory, thoracic and mediastinal disorders
Cough | 1 | 1 | 3 | 1
Pharyngolaryngeal pain | <1 | 0 | 2 | 1

Monotherapy versus Adjunctive Therapy

The designs of the two placebo-controlled, 6-week, double-blind trials in adult subjects with schizoaffective disorder included the option for subjects to receive antidepressants (except monoamine oxidase inhibitors) and/or mood stabilizers (lithium, valproate, or lamotrigine). In the subject population evaluated for safety, 230 (55%) subjects received INVEGA as monotherapy and 190 (45%) subjects received INVEGA as an adjunct to mood stabilizers and/or antidepressants. When comparing these 2 subpopulations, only nausea occurred at a greater frequency (≥ 3% difference) in subjects receiving INVEGA as monotherapy.

Discontinuations Due to Adverse Reactions

Schizophrenia Trials

The percentages of subjects who discontinued due to adverse reactions in the three schizophrenia placebo-controlled, 6-week, fixed-dose studies in adults were 3% and 1% in INVEGA- and placebo-treated subjects, respectively. The most common reasons for discontinuation were nervous system disorders (2% and 0% in INVEGA- and placebo-treated subjects, respectively).

Among the adverse reactions in the 6-week, fixed-dose, placebo-controlled study in adolescents with schizophrenia, only dystonia led to discontinuation (<1% of INVEGA-treated subjects).

Schizoaffective Disorder Trials

The percentages of subjects who discontinued due to adverse reactions in the two schizoaffective disorder placebo-controlled 6-week studies in adults were 1% and <1% in INVEGA- and placebo-treated subjects, respectively. The most common reasons for discontinuation were gastrointestinal disorders (1% and 0% in INVEGA- and placebo-treated subjects, respectively).

Dose-Related Adverse Reactions

Schizophrenia Trials

Based on the pooled data from the three placebo-controlled, 6-week, fixed-dose studies in adult subjects with schizophrenia, among the adverse reactions that occurred with a greater than 2% incidence in the subjects treated with INVEGA, the incidences of the following adverse reactions increased with dose: somnolence, orthostatic hypotension, akathisia, dystonia, extrapyramidal disorder, hypertonia, parkinsonism, and salivary hypersecretion. For most of these, the increased incidence was seen primarily at the 12 mg dose, and, in some cases, the 9 mg dose.

In the 6-week, fixed-dose, placebo-controlled study in adolescents with schizophrenia, among the adverse reactions that occurred with >2% incidence in the subjects treated with INVEGA, the incidences of the following adverse reactions increased with dose: tachycardia, akathisia, extrapyramidal symptoms, somnolence, and headache.

Schizoaffective Disorder Trials

In a placebo-controlled, 6-week, high- and low-dose study in adult subjects with schizoaffective disorder, akathisia, dystonia, dysarthria, myalgia, nasopharyngitis, rhinitis, cough, and pharyngolaryngeal pain occurred more frequently (i.e., a difference of at least 2%) in subjects who received higher doses of INVEGA compared with subjects who received lower doses.

Demographic Differences

An examination of population subgroups in the three placebo-controlled, 6-week, fixed-dose studies in adult subjects with schizophrenia and in the two placebo-controlled, 6-week studies in adult subjects with schizoaffective disorder did not reveal any evidence of clinically relevant differences in safety on the basis of gender or race alone; there was also no difference on the basis of age [see Use in Specific Populations (8.5)] .

Extrapyramidal Symptoms (EPS)

Pooled data from the three placebo-controlled, 6-week, fixed-dose studies in adult subjects with schizophrenia provided information regarding treatment-emergent EPS. Several methods were used to measure EPS: (1) the Simpson-Angus global score (mean change from baseline) which broadly evaluates Parkinsonism, (2) the Barnes Akathisia Rating Scale global clinical rating score (mean change from baseline) which evaluates akathisia, (3) use of anticholinergic medications to treat emergent EPS (Table 7), and (4) incidence of spontaneous reports of EPS (Table 8). For the Simpson-Angus Scale, spontaneous EPS reports and use of anticholinergic medications, there was a dose-related increase observed for the 9 mg and 12 mg doses. There was no difference observed between placebo and INVEGA 3 mg and 6 mg doses for any of these EPS measures.

Table 7. Treatment-Emergent Extrapyramidal Symptoms (EPS) Assessed by Incidence of Ratings Scales and Use of Anticholinergic Medication – Schizophrenia Studies in Adults
 | Percentage of Patients
 |  | INVEGA
 | Placebo | 3 mg once daily | 6 mg once daily | 9 mg once daily | 12 mg once daily
EPS Group | (N=355) | (N=127) | (N=235) | (N=246) | (N=242)
Parkinsonism [For Parkinsonism, percent of patients with Simpson-Angus global score > 0.3 (Global score defined as total sum of items score divided by the number of items)] | 9 | 11 | 3 | 15 | 14
Akathisia [For Akathisia, percent of patients with Barnes Akathisia Rating Scale global score ≥ 2] | 6 | 6 | 4 | 7 | 9
Use of anticholinergic medications [Percent of patients who received anticholinergic medications to treat emergent EPS] | 10 | 10 | 9 | 22 | 22

Table 8. Treatment-Emergent Extrapyramidal Symptoms (EPS)-Related Adverse Events by MedDRA Preferred Term – Schizophrenia Studies in Adults
 | Percentage of Patients
 |  | INVEGA
 | Placebo | 3 mg once daily | 6 mg once daily | 9 mg once daily | 12 mg once daily
EPS Group | (N=355) | (N=127) | (N=235) | (N=246) | (N=242)
Overall percentage of patients with EPS-related AE | 11 | 13 | 10 | 25 | 26
Dyskinesia | 3 | 5 | 3 | 8 | 9
Dystonia | 1 | 1 | 1 | 5 | 5
Hyperkinesia | 4 | 4 | 3 | 8 | 10
Parkinsonism | 2 | 3 | 3 | 7 | 6
Tremor | 3 | 3 | 3 | 4 | 3
Dyskinesia group includes: Dyskinesia, extrapyramidal disorder, muscle twitching, tardive dyskinesia
Dystonia group includes: Dystonia, muscle spasms, oculogyration, trismus
Hyperkinesia group includes: Akathisia, hyperkinesia
Parkinsonism group includes: Bradykinesia, cogwheel rigidity, drooling,
hypertonia, hypokinesia, muscle rigidity, musculoskeletal stiffness, parkinsonism
Tremor group includes: Tremor

Compared to data from the studies in adults subjects with schizophrenia, pooled data from the two placebo-controlled 6-week studies in adult subjects with schizoaffective disorder showed similar types and frequencies of EPS as measured by rating scales, anticholinergic medication use, and spontaneous reports of EPS-related adverse events. For subjects with schizoaffective disorder, there was no dose-related increase in EPS observed for parkinsonism with the Simpson-Angus scale or akathisia with the Barnes Akathisia Rating Scale. There was a dose-related increase observed with spontaneous EPS reports of hyperkinesia and dystonia and in the use of anticholinergic medications.

Table 9 shows the EPS data from the pooled schizoaffective disorder trials.

Table 9. Treatment-Emergent Extrapyramidal Symptoms (EPS)-Related Adverse Events by MedDRA Preferred Term – Schizoaffective Disorder Studies in Adults
 | Percentage of Patients
 |  | INVEGA
 | Placebo | 3–6 mg once-daily fixed-dose range | 9–12 mg once-daily fixed-dose range | 3–12 mg once-daily flexible dose
EPS Group | (N=202) | (N=108) | (N=98) | (N=214)
Overall percentage of patients with EPS-related AE | 11 | 23 | 22 | 17
Dyskinesia | 1 | 3 | 1 | 1
Dystonia | 1 | 2 | 3 | 2
Hyperkinesia | 5 | 5 | 8 | 7
Parkinsonism | 3 | 14 | 7 | 7
Tremor | 3 | 12 | 11 | 5
Dyskinesia group includes: Dyskinesia, muscle twitching
Dystonia group includes: Dystonia, muscle spasms, oculogyration
Hyperkinesia group includes: Akathisia, hyperkinesia, restlessness
Parkinsonism group includes: Bradykinesia, drooling, hypertonia, muscle rigidity, muscle tightness, musculoskeletal stiffness, parkinsonian gait, parkinsonism
Tremor group includes: Tremor

The incidences of EPS-related adverse events in the adolescent schizophrenia studies showed a similar dose-related pattern to those in the adult studies. There were notably higher incidences of dystonia, hyperkinesia, tremor, and parkinsonism in the adolescent population as compared to the adult studies (Table 10).

Table 10. Treatment-Emergent Extrapyramidal Symptoms (EPS)-Related Adverse Events by MedDRA Preferred Term – Schizophrenia Studies in Adolescent Subjects
 | Percentage of Patients
 |  | INVEGA
 | Placebo | 1.5 mg once daily | 3 mg once daily | 6 mg once daily | 12 mg once daily
EPS Group | (N=51) | (N=54) | (N=16) | (N=45) | (N=35)
Overall percentage of patients with EPS-related AE | 0 | 6 | 25 | 22 | 40
Hyperkinesia | 0 | 4 | 6 | 11 | 17
Dystonia | 0 | 2 | 0 | 11 | 14
Tremor | 0 | 2 | 6 | 7 | 11
Parkinsonism | 0 | 0 | 6 | 2 | 14
Dyskinesia | 0 | 2 | 6 | 2 | 6
Hyperkinesia group includes: Akathisia
Dystonia group includes: Dystonia, muscle contracture, oculogyric crisis, tongue paralysis, torticollis
Tremor group includes: Tremor
Parkinsonism group includes: Cogwheel rigidity, extrapyramidal disorder, muscle rigidity
Dyskinesia group includes: Dyskinesia, muscle contractions involuntary

Dystonia

Class Effect:Symptoms of dystonia, prolonged abnormal contractions of muscle groups, may occur in susceptible individuals during the first few days of treatment. Dystonic symptoms include: spasm of the neck muscles, sometimes progressing to tightness of the throat, swallowing difficulty, difficulty breathing, and/or protrusion of the tongue. While these symptoms can occur at low doses, they occur more frequently and with greater severity with high potency and at higher doses of first generation antipsychotic drugs. An elevated risk of acute dystonia is observed in males and younger age groups.

Laboratory Test Abnormalities

In the pooled data from the three placebo-controlled, 6-week, fixed-dose studies in adult subjects with schizophrenia and from the two placebo-controlled, 6-week studies in adult subjects with schizoaffective disorder, between-group comparisons revealed no medically important differences between INVEGA and placebo in the proportions of subjects experiencing potentially clinically significant changes in routine serum chemistry, hematology, or urinalysis parameters. Similarly, there were no differences between INVEGA and placebo in the incidence of discontinuations due to changes in hematology, urinalysis, or serum chemistry, including mean changes from baseline in fasting glucose, insulin, c-peptide, triglyceride, HDL, LDL, and total cholesterol measurements. However, INVEGA was associated with increases in serum prolactin [see Warnings and Precautions (5.7)].

Other Adverse Reactions Observed During Premarketing Evaluation of INVEGA

The following additional adverse reactions occurred in < 2% of INVEGA-treated subjects in the above schizophrenia and schizoaffective disorder clinical trial datasets. The following also includes additional adverse reactions reported at any frequency by INVEGA-treated subjects who participated in other clinical studies.

Cardiac disorders: bradycardia, palpitations

Eye disorders: eye movement disorder

Gastrointestinal disorders: flatulence

General disorders: edema

Immune system disorders: anaphylactic reaction

Infections and infestations: urinary tract infection

Investigations:alanine aminotransferase increased, aspartate aminotransferase increased

Musculoskeletal and connective tissue disorders: arthralgia, pain in extremity

Nervous system disorders: opisthotonus

Psychiatric disorders: agitation, insomnia, nightmare

Reproductive system and breast disorders: breast discomfort, menstruation irregular, retrograde ejaculation

Respiratory, thoracic and mediastinal disorders: nasal congestion

Skin and subcutaneous tissue disorders: pruritus, rash

Vascular disorders: hypertension

The safety of INVEGA was also evaluated in a long-term trial designed to assess the maintenance of effect with INVEGA in adults with schizophrenia [see Clinical Studies (14)] . In general, adverse reaction types, frequencies, and severities during the initial 14-week open-label phase of this study were comparable to those observed in the 6-week, placebo-controlled, fixed-dose studies. Adverse reactions reported during the long-term double-blind phase of this study were similar in type and severity to those observed in the initial 14-week open-label phase.

6.2 Postmarketing Experience

The following adverse reactions have been identified during postapproval use of INVEGA; because these reactions were reported voluntarily from a population of uncertain size, it is not possible to reliably estimate their frequency: angioedema, catatonia, ileus, priapism, somnambulism, swollen tongue, tardive dyskinesia, thrombotic thrombocytopenic purpura, urinary incontinence, urinary retention.

6.3 Adverse Reactions Reported with Risperidone

Paliperidone is the major active metabolite of risperidone. Adverse reactions reported with risperidone can be found in the ADVERSE REACTIONS section of the risperidone package insert.

7 DRUG INTERACTIONS

7.1 Potential for INVEGA to Affect Other Drugs

Given the primary CNS effects of paliperidone [see Adverse Reactions (6.1, 6.2)] , INVEGA should be used with caution in combination with other centrally acting drugs and alcohol. Paliperidone may antagonize the effect of levodopa and other dopamine agonists.

Because of its potential for inducing orthostatic hypotension, an additive effect may be observed when INVEGA is administered with other therapeutic agents that have this potential [see Warnings and Precautions (5.9)] .

Paliperidone is not expected to cause clinically important pharmacokinetic interactions with drugs that are metabolized by cytochrome P450 isozymes. In vitro studies in human liver microsomes showed that paliperidone does not substantially inhibit the metabolism of drugs metabolized by cytochrome P450 isozymes, including CYP1A2, CYP2A6, CYP2C8/9/10, CYP2D6, CYP2E1, CYP3A4, and CYP3A5. Therefore, paliperidone is not expected to inhibit clearance of drugs that are metabolized by these metabolic pathways in a clinically relevant manner. Paliperidone is also not expected to have enzyme inducing properties.

Paliperidone is a weak inhibitor of P-glycoprotein (P-gp) at high concentrations. No in vivo data are available and the clinical relevance is unknown.

Pharmacokinetic interaction between lithium and INVEGA is unlikely.

In a drug interaction study, co-administration of INVEGA (12 mg once daily for 5 days) with divalproex sodium extended-release tablets (500 mg to 2000 mg once daily) did not affect the steady-state pharmacokinetics (AUC24h and Cmax,ss) of valproate in 13 patients stabilized on valproate. In a clinical study, subjects on stable doses of valproate had comparable valproate average plasma concentrations when INVEGA 3–15 mg/day was added to their existing valproate treatment.

7.2 Potential for Other Drugs to Affect INVEGA

Paliperidone is not a substrate of CYP1A2, CYP2A6, CYP2C9, and CYP2C19, so that an interaction with inhibitors or inducers of these isozymes is unlikely. While in vitro studies indicate that CYP2D6 and CYP3A4 may be minimally involved in paliperidone metabolism, in vivo studies do not show decreased elimination by these isozymes and they contribute to only a small fraction of total body clearance. In vitro studies have shown that paliperidone is a P-gp substrate.

Co-administration of INVEGA 6 mg once daily with carbamazepine, a strong inducer of both CYP3A4 and P-glycoprotein (P-gp), at 200 mg twice daily caused a decrease of approximately 37% in the mean steady-state Cmax and AUC of paliperidone. This decrease is caused, to a substantial degree, by a 35% increase in renal clearance of paliperidone. A minor decrease in the amount of drug excreted unchanged in the urine suggests that there was little effect on the CYP metabolism or bioavailability of paliperidone during carbamazepine co-administration. On initiation of carbamazepine, the dose of INVEGA should be re-evaluated and increased if necessary. Conversely, on discontinuation of carbamazepine, the dose of INVEGA should be re-evaluated and decreased if necessary.

Paliperidone is metabolized to a limited extent by CYP2D6 [see Clinical Pharmacology (12.3)] . In an interaction study in healthy subjects in which a single 3 mg dose of INVEGA was administered concomitantly with 20 mg per day of paroxetine (a potent CYP2D6 inhibitor), paliperidone exposures were on average 16% (90% CI: 4, 30) higher in CYP2D6 extensive metabolizers. Higher doses of paroxetine have not been studied. The clinical relevance is unknown.

Co-administration of a single dose of INVEGA 12 mg with divalproex sodium extended-release tablets (two 500 mg tablets once daily) resulted in an increase of approximately 50% in the Cmax and AUC of paliperidone. Dosage reduction for INVEGA should be considered when INVEGA is co-administered with valproate after clinical assessment.

Pharmacokinetic interaction between lithium and INVEGA is unlikely.

8 USE IN SPECIFIC POPULATIONS

8.1 Pregnancy

Pregnancy Exposure Registry

There is a pregnancy exposure registry that monitors pregnancy outcomes in women exposed to atypical antipsychotics, including INVEGA, during pregnancy. Healthcare providers are encouraged to register patients by contacting the National Pregnancy Registry for Atypical Antipsychotics at 1-866-961-2388 or online at http://womensmentalhealth.org/clinical-and-research-programs/pregnancyregistry/.

Risk Summary

Neonates exposed to antipsychotic drugs during the third trimester of pregnancy are at risk for extrapyramidal and/or withdrawal symptoms following delivery (see Clinical Considerations) . Overall, available data from published epidemiologic studies of pregnant women exposed to paliperidone have not established a drug-associated risk of major birth defects, miscarriage, or adverse maternal or fetal outcomes (see Data) . There are risks to the mother associated with untreated schizophrenia and with exposure to antipsychotics, including INVEGA, during pregnancy (see Clinical Considerations).

The estimated background risk of major birth defects and miscarriage for the indicated population is unknown. All pregnancies have a background risk of birth defects, loss, or other adverse outcomes. In the U.S. general population, the estimated background risk of major birth defects and miscarriage in clinically recognized pregnancies is 2–4% and 15–20%, respectively.

In animal reproduction studies, there were no increases in fetal abnormalities when pregnant rats and rabbits were treated with paliperidone during the period of organogenesis with up to 8 times the maximum recommended human dose (MRHD) based on mg/m^2body surface area. Additional reproduction toxicity studies were conducted with orally administered risperidone, which is extensively converted to paliperidone (see Animal data).

Clinical Considerations

Disease-associated maternal and/or embryo/fetal risk

There is a risk to the mother from untreated schizophrenia, including increased risk of relapse, hospitalization, and suicide. Schizophrenia are associated with increased adverse perinatal outcomes, including preterm birth. It is not known if this is a direct result of the illness or other comorbid factors.

Fetal/Neonatal Adverse Reactions

Extrapyramidal and/or withdrawal symptoms, including agitation, hypertonia, hypotonia, tremor, somnolence, respiratory distress, and feeding disorder have been reported in neonates who were exposed to antipsychotic drugs, including INVEGA, during the third trimester of pregnancy. These symptoms have varied in severity. Monitor neonates for extrapyramidal and/or withdrawal symptoms and manage symptoms appropriately. Some neonates recovered within hours or days without specific treatment; others required prolonged hospitalization.

Data

Human Data

Published data from observational studies, birth registries, and case reports on the use of atypical antipsychotics during pregnancy do not report a clear association with antipsychotics and major birth defects. A prospective observational study including 6 women treated with risperidone, the parent compound of paliperidone, demonstrated placental passage of risperidone and paliperidone. A retrospective cohort study from a Medicaid database of 9258 women exposed to antipsychotics during pregnancy did not indicate an overall increased risk for major birth defects. There was a small increase in the risk of major birth defects (RR= 1.26, 95% CI 1.02–1.56) and of cardiac malformations (RR=1.26, 95% CI 0.88–1.81) in a subgroup of 1566 women exposed to the parent compound of paliperidone, risperidone, during the first trimester of pregnancy; however, there is no mechanism of action to explain the difference in malformation rates.

Animal Data

In animal reproduction studies, there were no increases in fetal abnormalities when pregnant rats and rabbits were treated with paliperidone during the period of organogenesis with up to 8 times the MRHD of 12 mg based on mg/m^2 body surface area.

Additional reproduction toxicity studies were conducted with orally administered risperidone, which is extensively converted to paliperidone. Cleft palate was observed in the offspring of pregnant mice treated with risperidone at 3 to 4 times the MRHD of 16 mg based on mg/m^2 body surface area; maternal toxicity occurred at 4 times the MHRD. There was no evidence of teratogenicity in embryo-fetal developmental toxicity studies with risperidone in rats and rabbits at doses up to 6 times the MRHD of 16 mg/day risperidone based on mg/m^2 body surface area. When the offspring of pregnant rats, treated with risperidone at 0.6 times the MRHD based on mg/m^2body surface area, reached adulthood, learning was impaired. Increased neuronal cell death occurred in the fetal brains of the offspring of pregnant rats treated at 0.5 to 1.2 times the MRHD; the postnatal development and growth of the offspring was delayed.

In rat reproduction studies with risperidone, pup deaths occurred at oral doses which are less than the MRHD of risperidone based on mg/m^2 body surface area; it is not known whether these deaths were due to a direct effect on the fetuses or pups or to effects on the dams (see RISPERDAL package insert).

8.2 Lactation

Risk Summary

Limited data from published literature report the presence of paliperidone in human breast milk. There is no information on the effects on the breastfed infant, or the effects on milk production; however, there are reports of sedation, failure to thrive, jitteriness, and extrapyramidal symptoms (tremors and abnormal muscle movements) in breastfed infants exposed to paliperidone's parent compound, risperidone (see Clinical Considerations) . The developmental and health benefits of breastfeeding should be considered along with the mother's clinical need for INVEGA and any potential adverse effects on the breastfed child from INVEGA or from the mother's underlying condition.

Clinical Considerations

Infants exposed to INVEGA through breastmilk should be monitored for excess sedation, failure to thrive, jitteriness, and extrapyramidal symptoms (tremors and abnormal muscle movements).

8.3 Females and Males of Reproductive Potential

Infertility

Females

Based on the pharmacologic action of paliperidone (D2 receptor antagonism), treatment with INVEGA may result in an increase in serum prolactin levels, which may lead to a reversible reduction in fertility in females of reproductive potential [see Warnings and Precautions (5.7)].

8.4 Pediatric Use

Safety and effectiveness of INVEGA in the treatment of schizophrenia were evaluated in 150 adolescent subjects 12–17 years of age with schizophrenia who received INVEGA in the dose range of 1.5 mg to 12 mg/day in a 6-week, double-blind, placebo-controlled trial.

Safety and effectiveness of INVEGA for the treatment of schizophrenia in patients < 12 years of age have not been established. Safety and effectiveness of INVEGA for the treatment of schizoaffective disorder in patients < 18 years of age have not been studied.

Juvenile Animal Studies

In a study in which juvenile rats were treated with oral paliperidone from days 24 to 73 of age, a reversible impairment of performance in a test of learning and memory was seen, in females only, with a no-effect dose of 0.63 mg/kg/day, which produced plasma levels (AUC) of paliperidone similar to those in adolescents at MRHD of 12 mg/day. No other consistent effects on neurobehavioral or reproductive development were seen up to the highest dose tested (2.5 mg/kg/day), which produced plasma levels of paliperidone 2–3 times those in adolescents.

Juvenile dogs were treated for 40 weeks with oral risperidone, which is extensively metabolized to paliperidone in animals and humans, at doses of 0.31, 1.25, or 5 mg/kg/day. Decreased bone length and density were seen with a no-effect dose of 0.31 mg/kg/day, which produced plasma levels (AUC) of risperidone plus paliperidone which were similar to those in children and adolescents receiving the MRHD of risperidone. In addition, a delay in sexual maturation was seen at all doses in both males and females. The above effects showed little or no reversibility in females after a 12-week drug-free recovery period.

The long-term effects of INVEGA on growth and sexual maturation have not been fully evaluated in children and adolescents.

8.5 Geriatric Use

The safety, tolerability, and efficacy of INVEGA were evaluated in a 6-week placebo-controlled study of 114 elderly subjects with schizophrenia (65 years of age and older, of whom 21 were 75 years of age and older). In this study, subjects received flexible doses of INVEGA (3 mg to 12 mg once daily). In addition, a small number of subjects 65 years of age and older were included in the 6-week placebo-controlled studies in which adult schizophrenic subjects received fixed doses of INVEGA (3 mg to 15 mg once daily) [see Clinical Studies (14)] . There were no subjects ≥ 65 years of age in the schizoaffective disorder studies.

Overall, of the total number of subjects in schizophrenia clinical studies of INVEGA (n=1796), including those who received INVEGA or placebo, 125 (7.0%) were 65 years of age and older and 22 (1.2%) were 75 years of age and older. No overall differences in safety or effectiveness were observed between these subjects and younger subjects, and other reported clinical experience has not identified differences in response between the elderly and younger patients, but greater sensitivity of some older individuals cannot be ruled out.

This drug is known to be substantially excreted by the kidney and clearance is decreased in patients with moderate to severe renal impairment [see Clinical Pharmacology (12.3)] , who should be given reduced doses. Because elderly patients are more likely to have decreased renal function, care should be taken in dose selection, and it may be useful to monitor renal function [see Dosage and Administration (2.5)] .

8.6 Renal Impairment

Dosing must be individualized according to the patient's renal function status [see Dosage and Administration (2.5)] .

8.7 Hepatic Impairment

No dosage adjustment is required in patients with mild to moderate hepatic impairment. INVEGA has not been studied in patients with severe hepatic impairment.

8.8 Patients with Parkinson's Disease or Lewy Body Dementia

Patients with Parkinson's Disease or Dementia with Lewy Bodies can experience increased sensitivity to INVEGA. Manifestations can include confusion, obtundation, postural instability with frequent falls, extrapyramidal symptoms, and clinical features consistent with neuroleptic malignant syndrome.

9 DRUG ABUSE AND DEPENDENCE

9.1 Controlled Substance

INVEGA (paliperidone) is not a controlled substance.

9.2 Abuse

Paliperidone has not been systematically studied in animals or humans for its potential for abuse. It is not possible to predict the extent to which a CNS-active drug will be misused, diverted, and/or abused once marketed. Consequently, patients should be evaluated carefully for a history of drug abuse, and such patients should be observed closely for signs of INVEGA misuse or abuse (e.g., development of tolerance, increases in dose, drug-seeking behavior).

9.3 Dependence

Paliperidone has not been systematically studied in animals or humans for its potential for tolerance or physical dependence.

10 OVERDOSAGE

10.1 Human Experience

While experience with paliperidone overdose is limited, among the few cases of overdose reported in pre-marketing trials, the highest estimated ingestion of INVEGA was 405 mg. Observed signs and symptoms included extrapyramidal symptoms and gait unsteadiness. Other potential signs and symptoms include those resulting from an exaggeration of paliperidone's known pharmacological effects, i.e., drowsiness and somnolence, tachycardia and hypotension, and QT prolongation. Torsade de pointes and ventricular fibrillation have been reported in a patient in the setting of overdose.

Paliperidone is the major active metabolite of risperidone. Overdose experience reported with risperidone can be found in the OVERDOSAGE section of the risperidone package insert.

10.2 Management of Overdosage

There is no specific antidote to paliperidone, therefore, appropriate supportive measures should be instituted and close medical supervision and monitoring should continue until the patient recovers. Consideration should be given to the extended-release nature of the product when assessing treatment needs and recovery. Multiple drug involvement should also be considered.

In case of acute overdose, establish and maintain an airway and ensure adequate oxygenation and ventilation. Administration of activated charcoal together with a laxative should be considered.

The possibility of obtundation, seizures, or dystonic reaction of the head and neck following overdose may create a risk of aspiration with induced emesis.

Cardiovascular monitoring should commence immediately, including continuous electrocardiographic monitoring for possible arrhythmias. If antiarrhythmic therapy is administered, disopyramide, procainamide, and quinidine carry a theoretical hazard of additive QT-prolonging effects when administered in patients with an acute overdose of paliperidone. Similarly, the alpha-blocking properties of bretylium might be additive to those of paliperidone, resulting in problematic hypotension.

Hypotension and circulatory collapse should be treated with appropriate measures, such as intravenous fluids and/or sympathomimetic agents (epinephrine and dopamine should not be used, since beta stimulation may worsen hypotension in the setting of paliperidone-induced alpha blockade). In cases of severe extrapyramidal symptoms, anticholinergic medication should be administered.

11 DESCRIPTION

INVEGA® contains paliperidone, an atypical antipsychotic belonging to the chemical class of benzisoxazole derivatives. INVEGA contains a racemic mixture of (+)- and (-)- paliperidone. The chemical name is (±)-3-[2-[4-(6-fluoro-1,2-benzisoxazol-3-yl)-1-piperidinyl]ethyl]-6,7,8,9-tetrahydro-9-hydroxy-2-methyl-4H-pyrido[1,2-a]pyrimidin-4-one. Its molecular formula is C23H27FN4O3and its molecular weight is 426.49. The structural formula is:

Paliperidone is sparingly soluble in 0.1N HCl and methylene chloride; practically insoluble in water, 0.1N NaOH, and hexane; and slightly soluble in N,N-dimethylformamide.

INVEGA (paliperidone) Extended-Release Tablets are intended for oral administration and are available in 3 mg (white), 6 mg (beige), and 9 mg (pink) strengths. INVEGA utilizes OROS® osmotic drug-release technology.

Inactive ingredients are carnauba wax, cellulose acetate, hydroxyethyl cellulose, propylene glycol, polyethylene glycol, polyethylene oxides, povidone, sodium chloride, stearic acid, butylated hydroxytoluene, hypromellose, titanium dioxide, and iron oxides. The 3 mg tablets also contain lactose monohydrate and triacetin.

Delivery System Components and Performance

INVEGA uses osmotic pressure to deliver paliperidone at a controlled rate. The delivery system, which resembles a capsule-shaped tablet in appearance, consists of an osmotically active trilayer core surrounded by a subcoat and semipermeable membrane. The trilayer core is composed of two drug layers containing the drug and excipients, and a push layer containing osmotically active components. There are two precision laser-drilled orifices on the drug-layer dome of the tablet. Each tablet strength has a different colored water-dispersible overcoat and print markings. In an aqueous environment, such as the gastrointestinal tract, the water-dispersible color overcoat erodes quickly. Water then enters the tablet through the semipermeable membrane that controls the rate at which water enters the tablet core, which, in turn, determines the rate of drug delivery. The hydrophilic polymers of the core hydrate and swell, creating a gel containing paliperidone that is then pushed out through the tablet orifices. The biologically inert components of the tablet remain intact during gastrointestinal transit and are eliminated in the stool as a tablet shell, along with insoluble core components.

12 CLINICAL PHARMACOLOGY

12.1 Mechanism of Action

Paliperidone is the major active metabolite of risperidone. The mechanism of action of paliperidone in schizophrenia is unclear. However, the drug's therapeutic effect in schizophrenia could be mediated through a combination of central dopamine Type 2 (D2) and serotonin Type 2 (5HT2A) receptor antagonism.

12.2 Pharmacodynamics

In vitro, paliperidone acts as an antagonist at the central dopamine Type 2 (D2) and serotonin Type 2 (5HT2A) receptors, with binding affinities (Ki values) of 1.6–2.8 nM for D2and 0.8–1.2 nM for 5HT2Areceptors. Paliperidone is also active as an antagonist at the α1and α2adrenergic receptors and H1histaminergic receptors, which may explain some of the other effects of the drug. Paliperidone has no affinity for cholinergic muscarinic or β1- and β2-adrenergic receptors. The pharmacological activity of the (+)- and (-)- paliperidone enantiomers is qualitatively and quantitatively similar in vitro.

12.3 Pharmacokinetics

Following a single dose, the plasma concentrations of paliperidone gradually rise to reach peak plasma concentration (Cmax) approximately 24 hours after dosing. The pharmacokinetics of paliperidone following INVEGA administration are dose-proportional within the available dose range. The terminal elimination half-life of paliperidone is approximately 23 hours.

Steady-state concentrations of paliperidone are attained within 4–5 days of dosing with INVEGA in most subjects. The mean steady-state peak:trough ratio for an INVEGA dose of 9 mg was 1.7 with a range of 1.2–3.1.

Following administration of INVEGA, the (+) and (-) enantiomers of paliperidone interconvert, reaching an AUC (+) to (-) ratio of approximately 1.6 at steady state.

Absorption and Distribution

The absolute oral bioavailability of paliperidone following INVEGA administration is 28%.

Administration of a 12 mg paliperidone extended-release tablet to healthy ambulatory subjects with a standard high-fat/high-caloric meal gave mean Cmax and AUC values of paliperidone that were increased by 60% and 54%, respectively, compared with administration under fasting conditions. Clinical trials establishing the safety and efficacy of INVEGA were carried out in subjects without regard to the timing of meals. While INVEGA can be taken without regard to food, the presence of food at the time of INVEGA administration may increase exposure to paliperidone [see Dosage and Administration (2.3)] .

Based on a population analysis, the apparent volume of distribution of paliperidone is 487 L. The plasma protein binding of racemic paliperidone is 74%.

Metabolism and Elimination

Although in vitro studies suggested a role for CYP2D6 and CYP3A4 in the metabolism of paliperidone, in vivo results indicate that these isozymes play a limited role in the overall elimination of paliperidone [see Drug Interactions (7)] .

One week following administration of a single oral dose of 1 mg immediate-release^14C-paliperidone to 5 healthy volunteers, 59% (range 51% – 67%) of the dose was excreted unchanged into urine, 32% (26% – 41%) of the dose was recovered as metabolites, and 6% – 12% of the dose was not recovered. Approximately 80% of the administered radioactivity was recovered in urine and 11% in the feces. Four primary metabolic pathways have been identified in vivo, none of which could be shown to account for more than 10% of the dose: dealkylation, hydroxylation, dehydrogenation, and benzisoxazole scission.

Population pharmacokinetic analyses found no difference in exposure or clearance of paliperidone between extensive metabolizers and poor metabolizers of CYP2D6 substrates.

Special Populations

Renal Impairment

The dose of INVEGA should be reduced in patients with moderate or severe renal impairment [see Dosage and Administration (2.5)] . The disposition of a single dose paliperidone 3 mg extended-release tablet was studied in adult subjects with varying degrees of renal function. Elimination of paliperidone decreased with decreasing estimated creatinine clearance. Total clearance of paliperidone was reduced in subjects with impaired renal function by 32% on average in mild (CrCl = 50 mL/min to < 80 mL/min), 64% in moderate (CrCl = 30 mL/min to < 50 mL/min), and 71% in severe (CrCl = 10 mL/min to < 30 mL/min) renal impairment, corresponding to an average increase in exposure (AUCinf) of 1.5 fold, 2.6 fold, and 4.8 fold, respectively, compared to healthy subjects. The mean terminal elimination half-life of paliperidone was 24 hours, 40 hours, and 51 hours in subjects with mild, moderate, and severe renal impairment, respectively, compared with 23 hours in subjects with normal renal function (CrCl ≥ 80 mL/min).

Hepatic Impairment

In a study in adult subjects with moderate hepatic impairment (Child-Pugh class B), the plasma concentrations of free paliperidone were similar to those of healthy subjects, although total paliperidone exposure decreased because of a decrease in protein binding. Consequently, no dose adjustment is required in patients with mild or moderate hepatic impairment. INVEGA has not been studied in patients with severe hepatic impairment.

Adolescents (12–17 years of age)

Paliperidone systemic exposure in adolescents weighing ≥ 51 kg (≥ 112 lbs) was similar to that in adults. In adolescents weighing < 51 kg (< 112 lbs), a 23% higher exposure was observed; this is considered not to be clinically significant. Age did not influence the paliperidone exposure.

Elderly

No dosage adjustment is recommended based on age alone. However, dose adjustment may be required because of age-related decreases in creatinine clearance [see Renal Impairment above and Dosage and Administration (2.1, 2.5)] .

Race

No dosage adjustment is recommended based on race. No differences in pharmacokinetics were observed in a pharmacokinetic study conducted in Japanese and Caucasians.

Gender

No dosage adjustment is recommended based on gender. No differences in pharmacokinetics were observed in a pharmacokinetic study conducted in men and women.

Smoking

No dosage adjustment is recommended based on smoking status. Based on in vitro studies utilizing human liver enzymes, paliperidone is not a substrate for CYP1A2; smoking should, therefore, not have an effect on the pharmacokinetics of paliperidone.

13 NONCLINICAL TOXICOLOGY

13.1 Carcinogenesis, Mutagenesis, Impairment of Fertility

Carcinogenesis

Carcinogenicity studies with paliperidone administered orally have not been performed.

Carcinogenicity studies with risperidone, which is extensively converted to paliperidone in rats, mice, and humans, were conducted in Swiss albino mice and Wistar rats. Risperidone was administered in the diet at daily doses of 0.63, 2.5, and 10 mg/kg for 18 months to mice and for 25 months to rats. A maximum tolerated dose was not achieved in male mice. There were statistically significant increases in pituitary gland adenomas, endocrine pancreas adenomas, and mammary gland adenocarcinomas. The no-effect dose for these tumors was less than or equal to the MRHD of risperidone based on mg/m^2body surface area (see risperidone package insert). An increase in mammary, pituitary, and endocrine pancreas neoplasms has been found in rodents after chronic administration of other antipsychotic drugs and is considered to be mediated by prolonged dopamine D2antagonism and hyperprolactinemia. The relevance of these tumor findings in rodents to human risk is unclear [see Warnings and Precautions (5.7)] .

Mutagenesis

No evidence of genotoxic potential for paliperidone was found in the Ames reverse mutation test, the mouse lymphoma assay, or the in vivo rat micronucleus test.

Impairment of Fertility

In a study of fertility, the percentage of treated female rats that became pregnant was not affected at oral doses of paliperidone of up to 2.5 mg/kg/day which is 2 times the MRHD based on mg/m^2body surface area. However, pre- and post-implantation loss was increased, and the number of live embryos was slightly decreased, at 2.5 mg/kg, a dose that also caused slight maternal toxicity. These parameters were not affected at a dose of 0.63 mg/kg, which is half of the MRHD based on mg/m^2body surface area.

The fertility of male rats was not affected at oral doses of paliperidone of up to 2 times the MRHD of 12 mg/day based on mg/m^2body surface area, although sperm count and sperm viability studies were not conducted with paliperidone. In a subchronic study in Beagle dogs with risperidone, which is extensively converted to paliperidone in dogs and humans, all doses tested (0.31 mg/kg – 5.0 mg/kg) resulted in decreases in serum testosterone and in sperm motility and concentration (0.6 to 10 times the MRHD of 16 mg/day for risperidone, based on mg/m^2body surface area). Serum testosterone and sperm parameters partially recovered, but remained decreased after the last observation (two months after treatment was discontinued).

14 CLINICAL STUDIES

14.1 Schizophrenia

Adults

The acute efficacy of INVEGA (3 mg to 15 mg once daily) was established in three placebo-controlled and active-controlled (olanzapine), 6-week, fixed-dose trials in non-elderly adult subjects (mean age of 37) who met DSM-IV criteria for schizophrenia. Studies were carried out in North America, Eastern Europe, Western Europe, and Asia. The doses studied among these three trials included 3 mg/day, 6 mg/day, 9 mg/day, 12 mg/day, and 15 mg/day. Dosing was in the morning without regard to meals.

Efficacy was evaluated using the Positive and Negative Syndrome Scale (PANSS), a validated multi-item inventory composed of five factors to evaluate positive symptoms, negative symptoms, disorganized thoughts, uncontrolled hostility/excitement, and anxiety/depression. Efficacy was also evaluated using the Personal and Social Performance (PSP) scale. The PSP is a validated clinician-rated scale that measures personal and social functioning in the domains of socially useful activities (e.g., work and study), personal and social relationships, self-care, and disturbing and aggressive behaviors.

In all 3 studies (n=1665), INVEGA was superior to placebo on the PANSS at all doses. Mean effects at all doses were fairly similar, although the higher doses in all studies were numerically superior. INVEGA was also superior to placebo on the PSP in these trials.

An examination of population subgroups did not reveal any evidence of differential responsiveness on the basis of gender, age (there were few patients over 65), or geographic region. There were insufficient data to explore differential effects based on race.

In a longer-term trial, adult outpatients meeting DSM-IV criteria for schizophrenia who had clinically responded (defined as PANSS score ≤ 70 or ≤ 4 on pre-defined PANSS subscales, as well as having been on a stable fixed dose of INVEGA for the last two weeks of an 8-week run-in phase) were entered into a 6-week open-label stabilization phase where they received INVEGA (doses ranging from 3 mg to 15 mg once daily). After the stabilization phase, patients were randomized in a double-blind manner to either continue on INVEGA at their achieved stable dose, or to placebo, until they experienced a relapse of schizophrenia symptoms. Relapse was pre-defined as significant increase in PANSS (or pre-defined PANSS subscales), hospitalization, clinically significant suicidal or homicidal ideation, or deliberate injury to self or others. An interim analysis of the data showed a significantly longer time to relapse in patients treated with INVEGA compared to placebo, and the trial was stopped early because maintenance of efficacy was demonstrated.

Adolescents

The efficacy of INVEGA in adolescent subjects with schizophrenia was established in a randomized, double-blind, parallel-group, placebo-controlled, 6-week study using a fixed-dose weight-based treatment group design over the dose range of 1.5 to 12 mg/day. The study was carried out in the US, India, Romania, Russia, and Ukraine, and involved subjects 12–17 years of age meeting DSM-IV criteria for schizophrenia, with diagnosis confirmation using the Kiddie Schedule for Affective Disorders and Schizophrenia-Present and Lifetime Version (K-SADS-PL).

Eligible subjects were randomly assigned to 1 of 4 treatment groups: a placebo group or INVEGA Low, Medium, or High dose groups. Doses were administered based on body weight to minimize the risk of exposing lower-weight adolescents to high doses of INVEGA. Subjects weighing between 29 kg and less than 51 kg at the baseline visit were randomly assigned to receive placebo or 1.5 mg (Low dose), 3 mg (Medium dose), or 6 mg (High dose) of INVEGA daily, and subjects weighing at least 51 kg at the baseline visit were randomly assigned to receive placebo or 1.5 mg (Low dose), 6 mg (Medium dose), or 12 mg (High dose) of INVEGA daily. Dosing was in the morning without regard to meals.

Efficacy was evaluated using PANSS. Overall, this study demonstrated the efficacy of INVEGA in adolescents with schizophrenia in the dose range of 3 to 12 mg/day. Doses within this broad range were shown to be effective, however, there was no clear enhancement to efficacy at the higher doses, i.e., 6 mg for subjects weighing less than 51 kg and 12 mg for subjects weighing 51 kg or greater. Although paliperidone was adequately tolerated within the dose range of 3 to 12 mg/day, adverse events were dose related.

14.2 Schizoaffective Disorder

Adults

The acute efficacy of INVEGA (3 mg to 12 mg once daily) in the treatment of schizoaffective disorder was established in two placebo-controlled, 6-week trials in non-elderly adult subjects. Enrolled subjects 1) met DSM-IV criteria for schizoaffective disorder, as confirmed by the Structured Clinical Interview for DSM-IV Disorders, 2) had a Positive and Negative Syndrome Scale (PANSS) total score of at least 60, and 3) had prominent mood symptoms as confirmed by a score of at least 16 on the Young Mania Rating Scale and/or Hamilton Rating Scale for Depression. The population included subjects with schizoaffective bipolar and depressive types. In one of these trials, efficacy was assessed in 211 subjects who received flexible doses of INVEGA (3–12 mg once daily). In the other study, efficacy was assessed in 203 subjects who were assigned to one of two dose levels of INVEGA: 6 mg with the option to reduce to 3 mg (n=105) or 12 mg with the option to reduce to 9 mg (n=98) once daily. Both studies included subjects who received INVEGA either as monotherapy [no mood stabilizers and/or antidepressants (55%)] or as an adjunct to mood stabilizers and/or antidepressants (45%). The most commonly used mood stabilizers were valproate and lithium. The most commonly used antidepressants were SSRIs and SNRIs. INVEGA was dosed in the morning without regard to meals. Studies were carried out in the United States, Eastern Europe, Russia, and Asia.

Efficacy was evaluated using the PANSS, a validated multi-item inventory composed of five factors to evaluate positive symptoms, negative symptoms, disorganized thoughts, uncontrolled hostility/excitement, and anxiety/depression. As secondary outcomes, mood symptoms were evaluated using the Hamilton Depression Rating Scale (HAM-D-21) and the Young Mania Rating Scale (YMRS).

The INVEGA group in the flexible-dose study (dosed between 3 and 12 mg/day, mean modal dose of 8.6 mg/day) and the higher dose group of INVEGA in the 2 dose-level study (12 mg/day with option to reduce to 9 mg/day) were each superior to placebo in the PANSS. Numerical improvements in mood symptoms were also observed, as measured by the HAM-D-21 and YMRS. In the lower dose group of the 2 dose-level study (6 mg/day with option to reduce to 3 mg/day), INVEGA was not significantly different from placebo as measured by the PANSS.

Taking the results of both studies together, INVEGA improved the symptoms of schizoaffective disorder at endpoint relative to placebo when administered either as monotherapy or as an adjunct to mood stabilizers and/or antidepressants. An examination of population subgroups did not reveal any evidence of differential responsiveness on the basis of gender, age, or geographic region. There were insufficient data to explore differential effects based on race.

16 HOW SUPPLIED/STORAGE AND HANDLING

INVEGA® (paliperidone) Extended-Release Tablets are available in the following strengths and packages. All tablets are capsule-shaped.

3 mg tablets are white and imprinted with "PAL 3", and are available in bottles of 30 (NDC 50458-550-01) and hospital unit dose packs of 100 (NDC 50458-550-10).

6 mg tablets are beige and imprinted with "PAL 6", and are available in bottles of 30 (NDC 50458-551-01) and hospital unit dose packs of 100 (NDC 50458-551-10).

9 mg tablets are pink and imprinted with "PAL 9", and are available in bottles of 30 (NDC 50458-552-01) and hospital unit dose packs of 100 (NDC 50458-552-10).

Storage and Handling

Store up to 25 °C (77 °F); excursions permitted to 15 °C to 30 °C (59 °F to 86 °F) [see USP Controlled Room Temperature]. Protect from moisture.

Keep out of reach of children.

17 PATIENT COUNSELING INFORMATION

Physicians are advised to discuss the following issues with patients for whom they prescribe INVEGA.

Neuroleptic Malignant Syndrome (NMS)

Counsel patients about a potentially fatal adverse reaction, Neuroleptic Malignant Syndrome (NMS), that has been reported in association with administration of antipsychotic drugs. Advise patients, family members, or caregivers to contact their healthcare provider or report to the emergency room if they experience signs and symptoms of NMS, including hyperpyrexia, muscle rigidity, altered mental status including delirium, and evidence of autonomic instability (irregular pulse or blood pressure, tachycardia, diaphoresis, and cardiac dysrhythmia) [see Warnings and Precautions (5.3)].

Tardive Dyskinesia

Counsel patients on the signs and symptoms of tardive dyskinesia and to contact their healthcare provider if these abnormal movements occur [see Warnings and Precautions (5.5)].

Metabolic Changes

Educate patients about the risk of metabolic changes, how to recognize symptoms of hyperglycemia and diabetes mellitus, and the need for specific monitoring, including blood glucose, lipids, and weight [see Warnings and Precautions (5.6)].

Orthostatic Hypotension

Educate patients about the risk of orthostatic hypotension and syncope, particularly at the time of initiating treatment, re-initiating treatment, or increasing the dose [see Warnings and Precautions (5.9)] .

Leukopenia/Neutropenia

Advise patients with a pre-existing low WBC or a history of drug-induced leukopenia/neutropenia they should have their CBC monitored while taking INVEGA [see Warnings and Precautions (5.11)] .

Hyperprolactinemia

Counsel patients on signs and symptoms of hyperprolactinemia that may be associated with chronic use of INVEGA. Advise them to seek medical attention if they experience any of the following: amenorrhea or galactorrhea in females, erectile dysfunction or gynecomastia in males [see Warnings and Precautions (5.7)] .

Interference with Cognitive and Motor Performance

Caution patients about performing activities requiring mental alertness, such as operating hazardous machinery, or operating a motor vehicle, until they are reasonably certain that INVEGA therapy does not affect them adversely [see Warnings and Precautions (5.12)] .

Priapism

Advise patients of the possibility of painful or prolonged penile erections (priapism). Instruct the patient to seek immediate medical attention in the event of priapism [see Warnings and Precautions (5.15)] .

Heat Exposure and Dehydration

Counsel patients on the importance of avoiding overheating and dehydration [see Warnings and Precautions (5.16)] .

Concomitant Medication

Advise patients to inform their healthcare providers if they are taking, or plan to take, any prescription or over-the-counter drugs, as there is a potential for interactions [see Drug Interactions (7)] .

Alcohol

Advise patients to avoid alcohol while taking INVEGA [see Drug Interactions (7.1)] .

Administration

Patients should be informed that INVEGA should be swallowed whole with the aid of liquids. Tablets should not be chewed, divided, or crushed. The medication is contained within a nonabsorbable shell designed to release the drug at a controlled rate. The tablet shell, along with insoluble core components, is eliminated from the body; patients should not be concerned if they occasionally notice something that looks like a tablet in their stool [see Dosage and Administration (2.3)] .

Pregnancy

Advise patients to notify their healthcare provider if they become pregnant or intend to become pregnant during treatment with INVEGA. Advise patients that INVEGA may cause extrapyramidal and/or withdrawal symptoms in a neonate. Advise patients that there is a pregnancy registry that monitors pregnancy outcomes in women exposed to INVEGA during pregnancy [see Use in Specific Populations (8.1)] .

Lactation

Advise breastfeeding women using INVEGA to monitor infants for somnolence, failure to thrive, jitteriness, and extrapyramidal symptoms (tremors and abnormal muscle movements) and to seek medical care if they notice these signs [see Use in Specific Populations (8.2)] .

Infertility

Advise females of reproductive potential that INVEGA may impair fertility due to an increase in serum prolactin levels. The effects on fertility are reversible [see Use in Specific Populations (8.3)].

INVEGA (paliperidone) Extended-Release Tablets

Manufactured for:
Janssen Pharmaceuticals, Inc.
Titusville, NJ 08560, USA

OROS is a registered trademark of ALZA Corporation

For patent information: www.janssenpatents.com

© Johnson & Johnson and its affiliates 2007

PRINCIPAL DISPLAY PANEL - 3 mg Tablet Bottle Label

NDC 50458-550-01

INVEGA®
PALIPERIDONE
Extended-Release Tablets

3 mg

Tablets should be swallowed whole.
Do not divide, crush, or chew.
Invega should be taken once daily.

Rx only

30 Tablets

janssen

PRINCIPAL DISPLAY PANEL - 6 mg Tablet Bottle Label

NDC 50458-551-01

INVEGA®
PALIPERIDONE
Extended-Release Tablets

6 mg

Tablets should be swallowed whole.
Do not divide, crush, or chew.
Invega should be taken once daily.

Rx only

30 Tablets

janssen

PRINCIPAL DISPLAY PANEL - 9 mg Tablet Bottle Label

NDC 50458-552-01

INVEGA®
PALIPERIDONE
Extended-Release Tablets

9 mg

Tablets should be swallowed whole.
Do not divide, crush, or chew.
Invega should be taken once daily.

Rx only

30 Tablets

janssen

PRINCIPAL DISPLAY PANEL - 1.5 mg Tablet Bottle Label

NDC 50458-554-01

INVEGA®
PALIPERIDONE
Extended-Release Tablets

1.5 mg

Tablets should be swallowed whole.
Do not divide, crush, or chew.
Invega should be taken once daily.

Rx only

30 Tablets

janssen